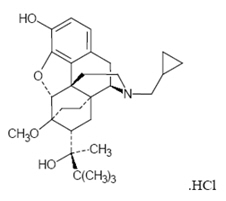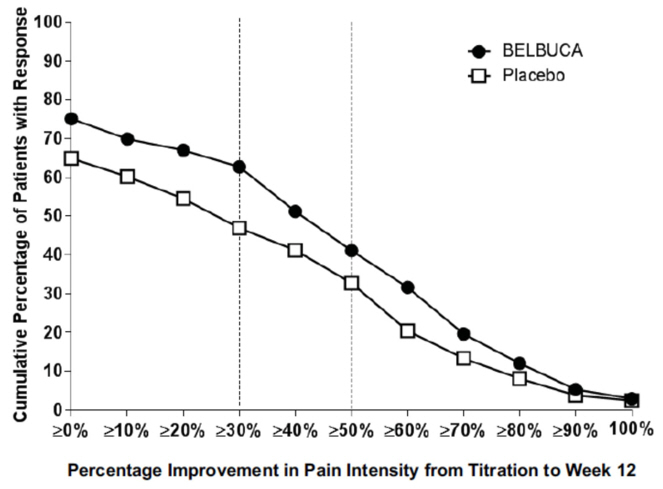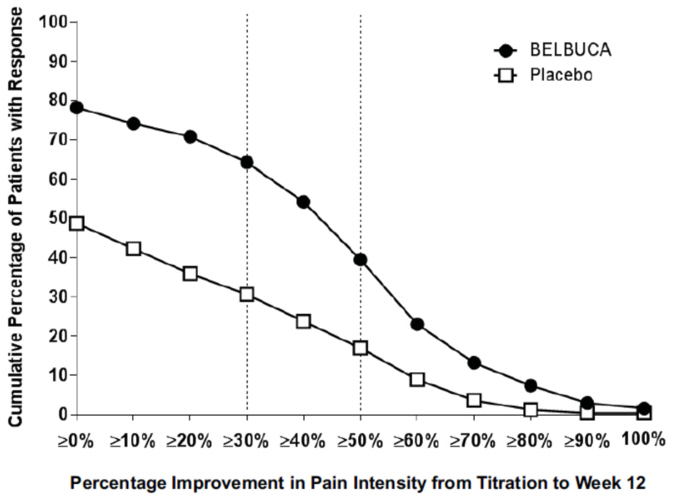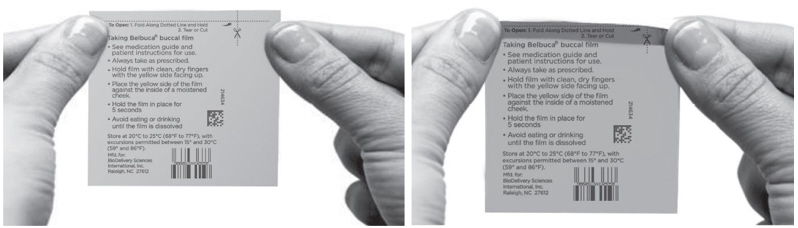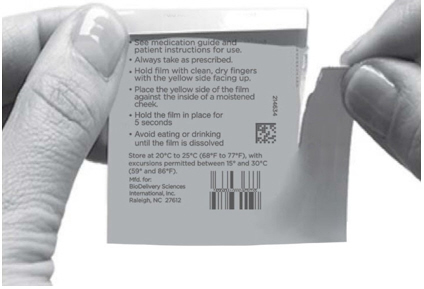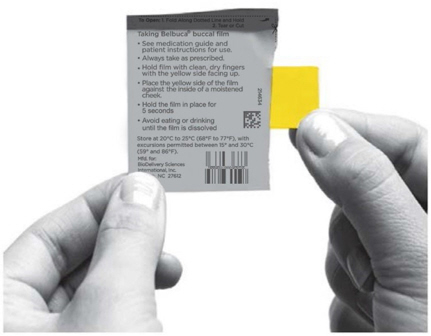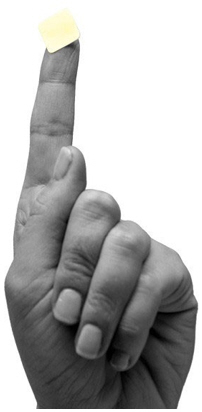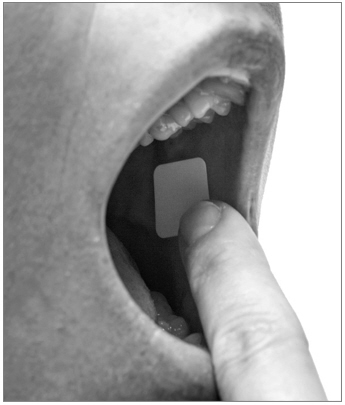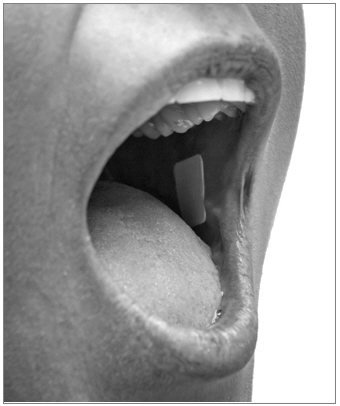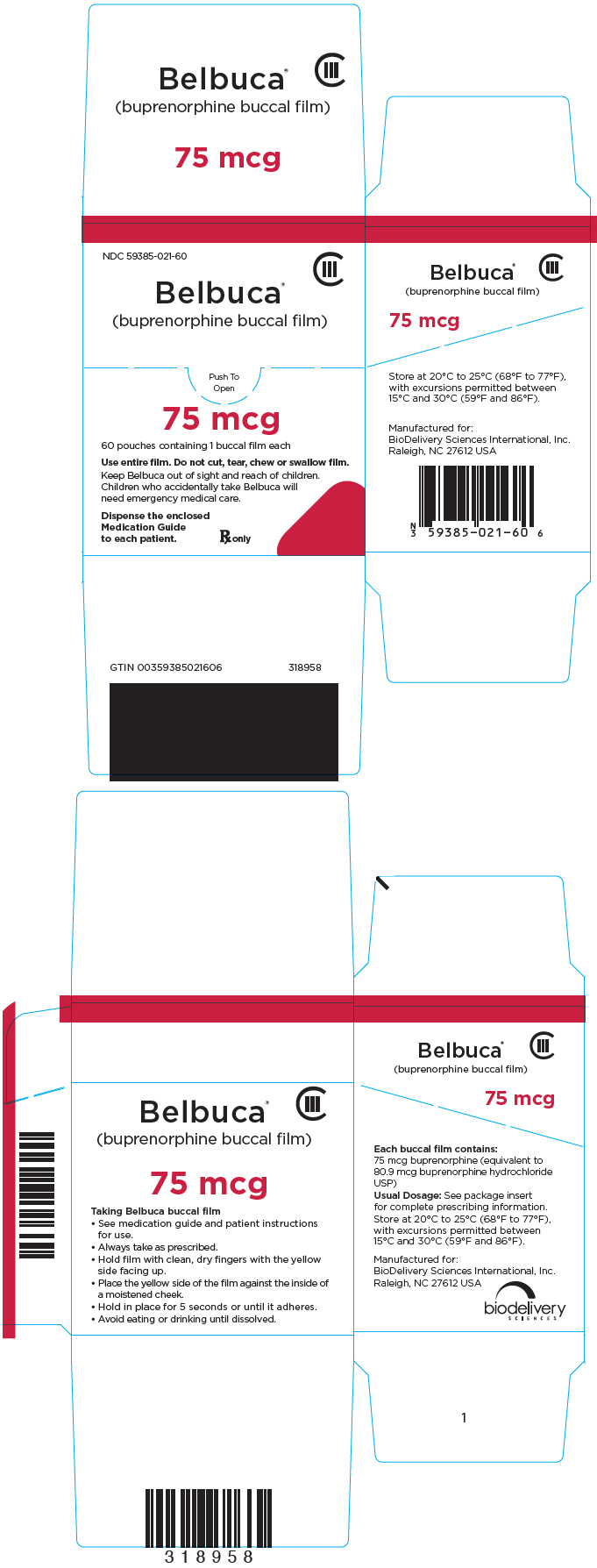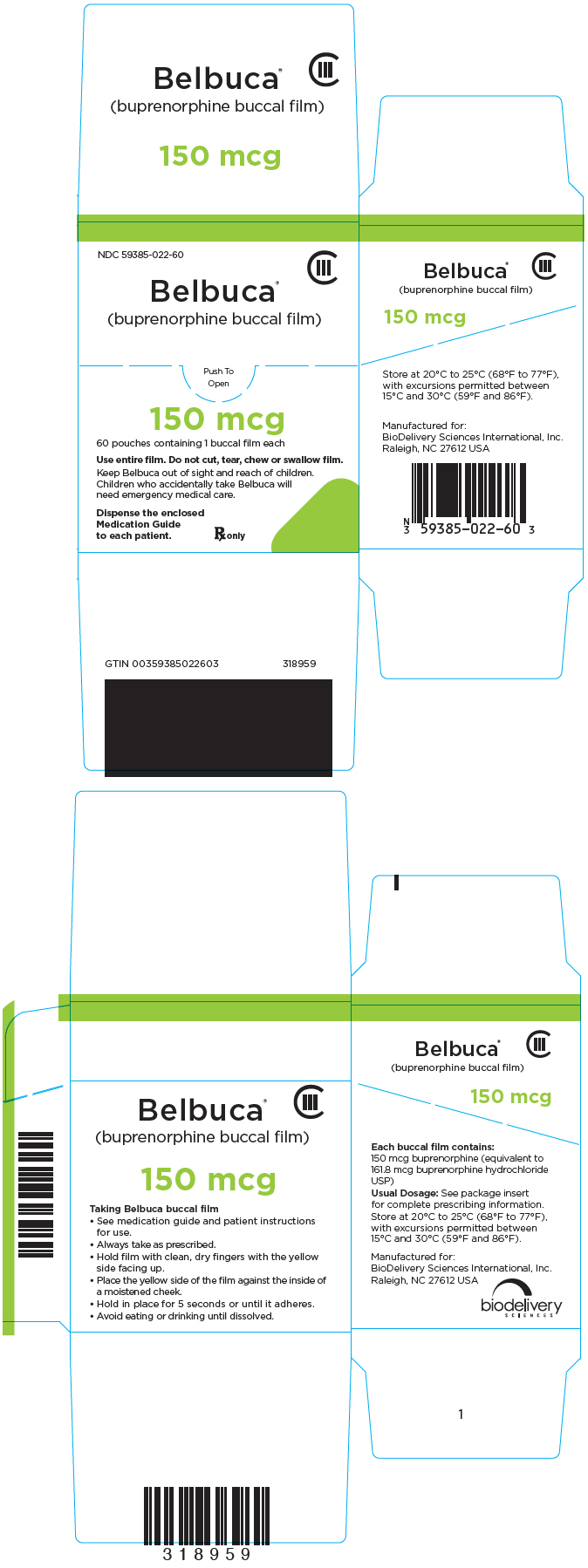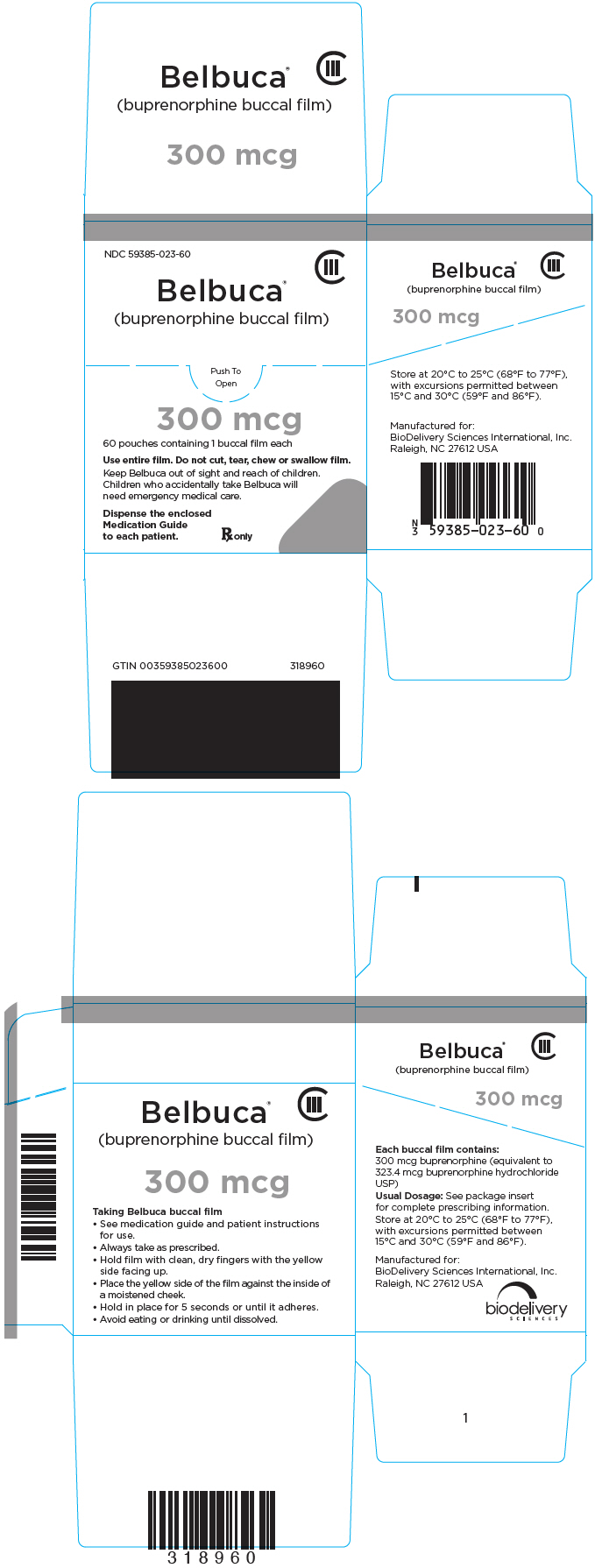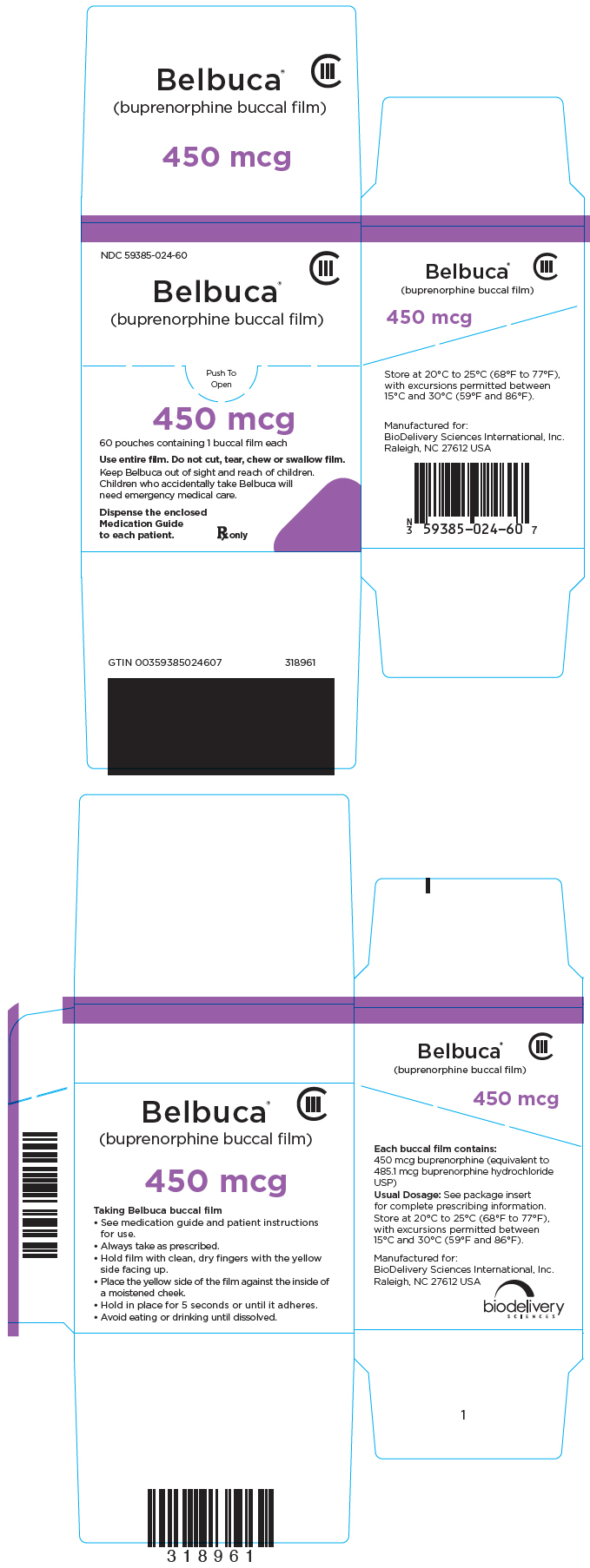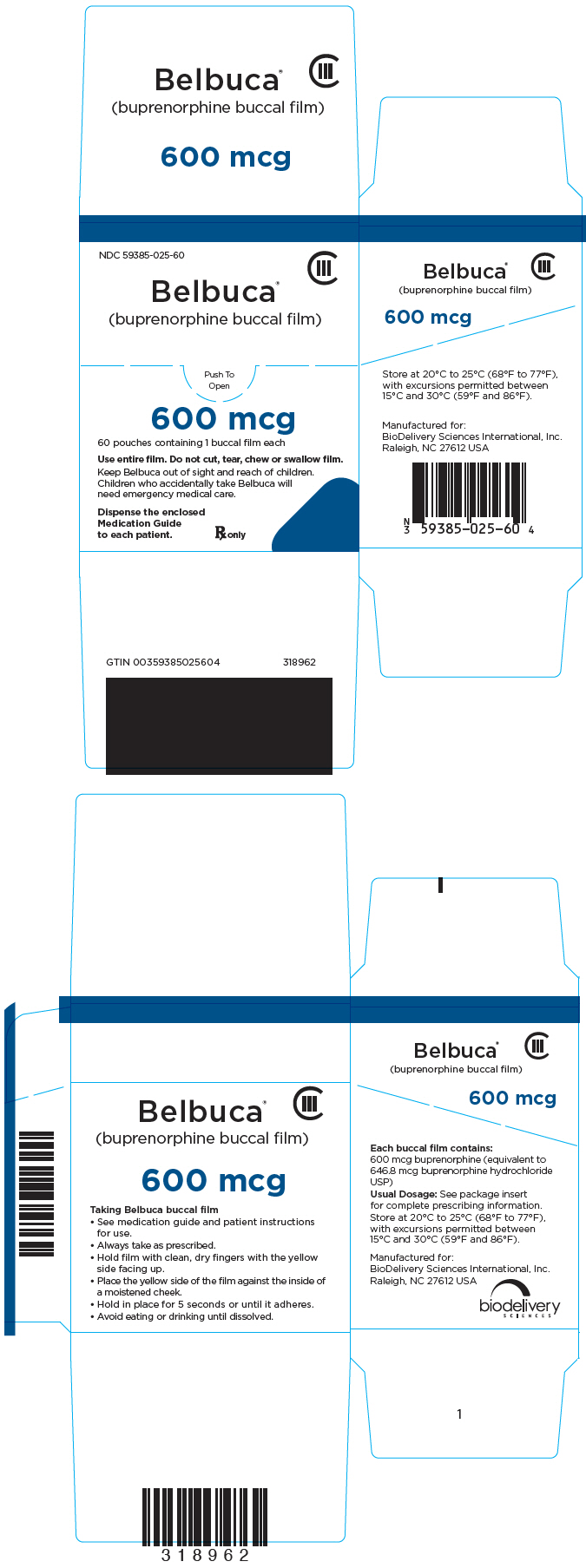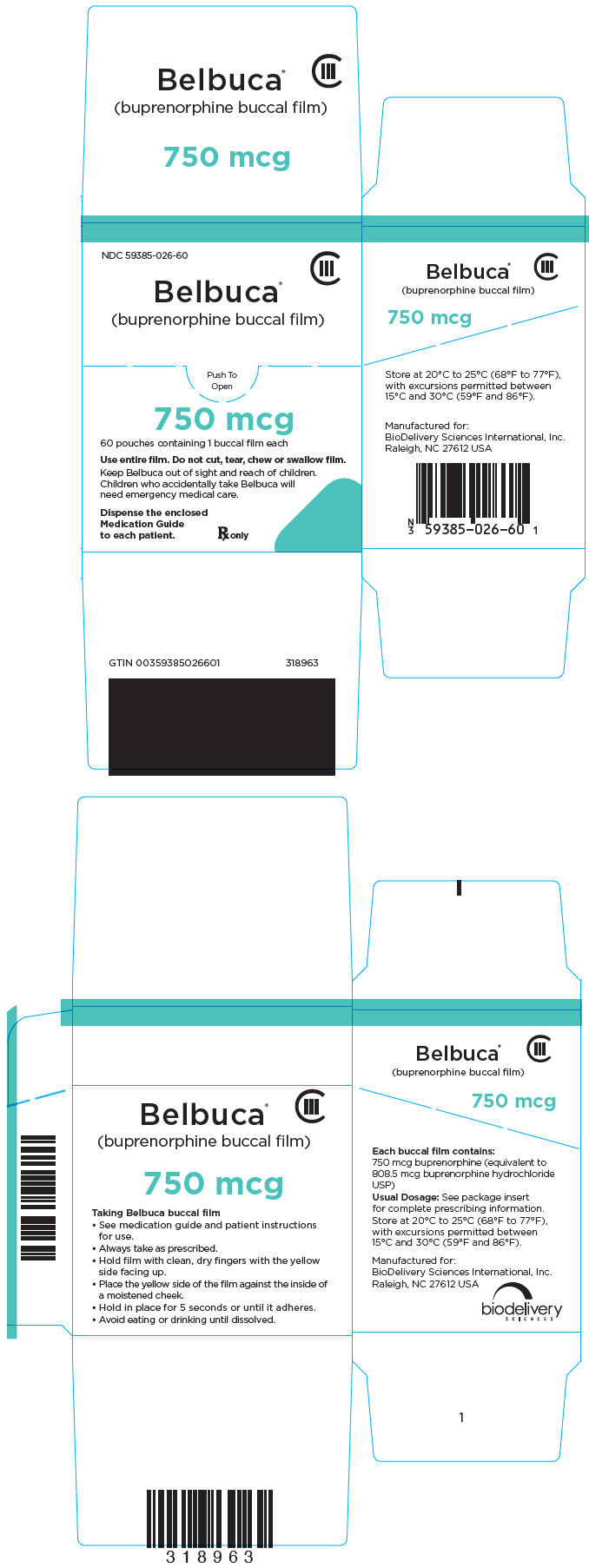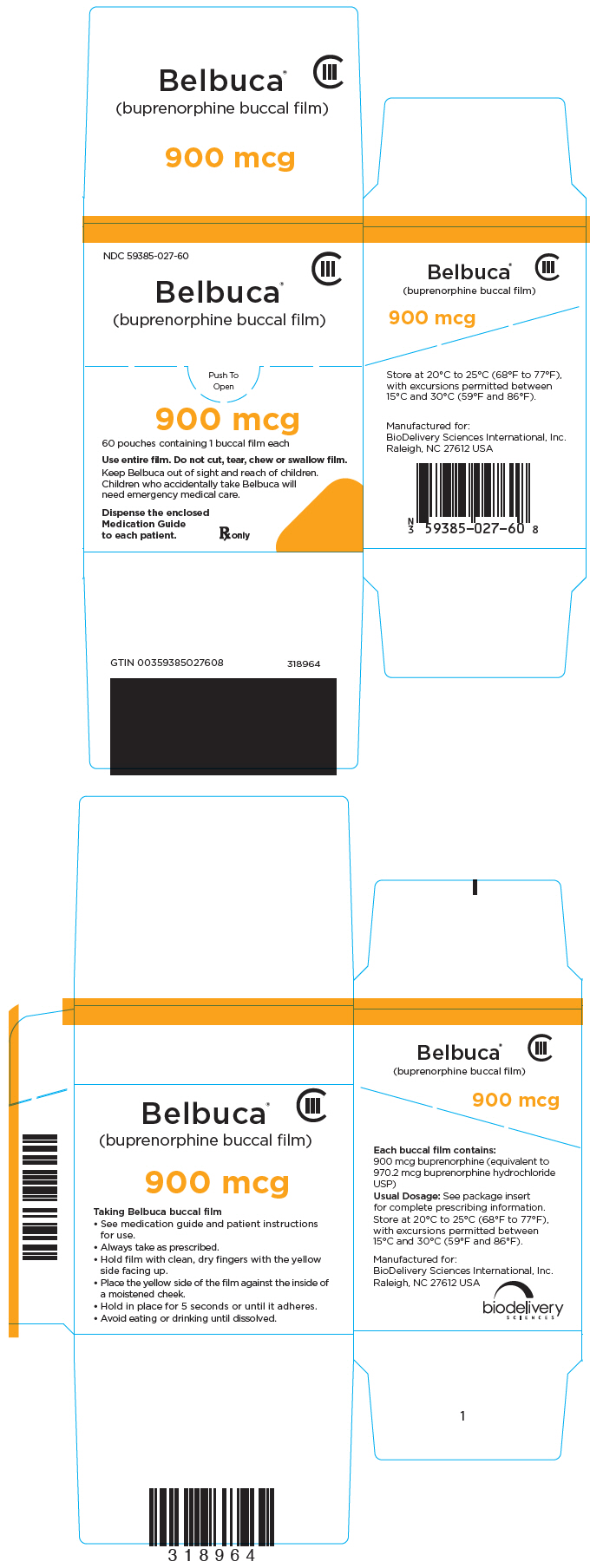 DRUG LABEL: BELBUCA
NDC: 59385-021 | Form: FILM, SOLUBLE
Manufacturer: BioDelivery Sciences International Inc
Category: prescription | Type: HUMAN PRESCRIPTION DRUG LABEL
Date: 20260102
DEA Schedule: CIII

ACTIVE INGREDIENTS: buprenorphine hydrochloride 75 ug/1 1
INACTIVE INGREDIENTS: HYDROXYETHYL CELLULOSE (280 MPA.S AT 5%); Titanium Dioxide; Peppermint Oil; Propylene Glycol; Sodium Benzoate; Methylparaben; Propylparaben; Ferric Oxide Yellow; ANHYDROUS CITRIC ACID; .ALPHA.-TOCOPHEROL ACETATE; SODIUM PHOSPHATE, MONOBASIC, ANHYDROUS; Sodium Hydroxide; Polycarbophil; HYDROXYPROPYL CELLULOSE (90000 WAMW); CARBOXYMETHYLCELLULOSE SODIUM (0.7 CARBOXYMETHYL SUBSTITUTION PER SACCHARIDE; 38 MPA.S AT 2%); Saccharin Sodium

HIGHLIGHTS OF PRESCRIBING INFORMATION

These highlights do not include all the information needed to use BELBUCA safely and effectively. See full prescribing information for BELBUCA.
BELBUCA® (buprenorphine buccal film), CIII
Initial U.S. Approval: 1981

WARNING: SERIOUS AND LIFE-THREATENING RISKS FROM USE OF BELBUCA

WARNING: SERIOUS LIFE-THREATENING RISKS FROM USE OF BELBUCA

See full prescribing information for complete boxed warning.

- BELBUCA exposes users to risks of addiction, abuse, and misuse, which can lead to overdose and death. Assess patient's risk before prescribing and reassess regularly for these behaviors and conditions. (5.1)
- Serious, life-threatening, or fatal respiratory depression may occur, especially during initiation or following a dosage increase. To reduce the risk of respiratory depression, proper dosing and titration of BELBUCA are essential. Instruct patients on proper administration of BELBUCA to reduce the risk. (2.1, 2.8, 5.2)
- Accidental exposure to BELBUCA, especially in children, can result in fatal overdose of buprenorphine. (5.2)
- Concomitant use of opioids with benzodiazepines or other central nervous system (CNS) depressants, including alcohol, may result in profound sedation, respiratory depression, coma, and death. Reserve concomitant prescribing for use in patients for whom alternative treatment options are inadequate. (5.3, 7)
- Advise pregnant women using opioids for an extended period of time of the risk of Neonatal Opioid Withdrawal Syndrome, which may be life-threatening if not recognized and treated. Ensure that management by neonatology experts will be available at delivery. (5.4)
- Healthcare providers are strongly encouraged to complete a REMS-compliant education program and to counsel patients and caregivers on serious risks, safe use, and the importance of reading the Medication Guide with each prescription. (5.5)

RECENT MAJOR CHANGES

Boxed Warning | 12/2025
Indications and Usage (1) | 12/2025
Dosage and Administration (2.2, 2.3, 2.5) | 12/2025
Warnings and Precautions (5.1, 5.2, 5.3, 5.12, 5.17) | 12/2025

1 INDICATIONS AND USAGE

BELBUCA buccal film contains buprenorphine, a partial opioid agonist. BELBUCA is indicated for the management of severe and persistent pain that requires an opioid analgesic that cannot be adequately treated with alternative options, including immediate-release opioids. (1)

Limitations of Use

- Because of the risks of addiction, abuse, misuse, overdose, and death, which can occur at any dosage or duration and persist over the course of therapy, reserve opioid analgesics, including BELBUCA, for use in patients for whom alternative treatment are ineffective, not tolerated, or would be otherwise inadequate to provide sufficient management of pain. (1, 5.1)
- BELBUCA is not indicated as an as-needed (prn) analgesic. (1)

2 DOSAGE AND ADMINISTRATION

- BELBUCA should be prescribed only by healthcare professionals who are knowledgeable about the use of extended-release/long-acting opioids and how to mitigate the associated risks. (2.1)
- Use the lowest effective dosage for the shortest duration of time consistent with individual patient treatment goals. Reserve titration to higher doses of BELBUCA for patients in whom lower doses are insufficiently effective and in whom the expected benefits of using a higher dose opioid clearly outweigh the substantial risks (2.1, 5)
- Initiate the dosing regimen for each patient individually, taking into account the patient's underlying cause and severity of pain, prior analgesic treatment and response, and risk factors for addiction, abuse, and misuse. (2.1, 5.1)
- Respiratory depression can occur at any time during opioid therapy, especially when initiating and following dosage increases with BELBUCA. Consider this risk when selecting an initial dose and when making dose adjustments. (2.1, 5.2).
- Discuss opioid overdose reversal agents and options for acquiring them with the patient and/or caregiver, both when initiating and renewing treatment with BELBUCA, especially if the patient has additional risk factors for overdose, or close contacts at risk for exposure and overdose. (2.2, 5.1, 5.2, 5.3)
- BELBUCA buccal film is for oral buccal use only and is to be applied to the buccal mucosa once daily or every 12 hours. (2.1)
- Patients who are not Opioid Tolerant: Initiate therapy with 75 mcg BELBUCA once daily or every 12 hours, as tolerated, for at least 4 days before increasing dose to 150 mcg every 12 hours. (2.3)
- Conversion from Other Opioid Analgesics to BELBUCA: Taper current daily opioid dose to 30 mg oral morphine sulfate equivalents (MSE) or less prior to initiating therapy with BELBUCA. (2.3)
  - For patients taking less than 30 mg oral MSE, initiate therapy with 75 mcg once daily or every 12 hours. (2.3)
  - For patients taking between 30 mg and 89 mg oral MSE, initiate therapy with 150 mcg BELBUCA every 12 hours following analgesic taper. (2.3)
  - For patients taking between 90 mg and 160 mg oral MSE, initiate therapy with 300 mcg BELBUCA every 12 hours following analgesic taper. (2.3)
  - For patients taking greater than 160 mg oral MSE, consider alternate analgesic. (2.3)
- BELBUCA doses of 600 mcg, 750 mcg, and 900 mcg are only for use following titration from lower doses of BELBUCA. (2.3)
- Patients with Severe Hepatic Impairment: Reduce the starting and incremental dose by half that of patients with normal liver function. (2.6, 5.19, 8.6)
- Patients with Oral Mucositis: Reduce the starting and incremental dose by half that of patients without mucositis. (2.7, 5.20)
- Periodically reassess patients receiving BELBUCA to evaluate the continued need for opioid analgesics to maintain pain control, for the signs or symptoms of adverse reactions, and for the development of addiction, abuse, or misuse. (2.4)
- Do not rapidly reduce or abruptly discontinue BELBUCA in a physically-dependent patient because rapid reduction or abrupt discontinuation of opioid analgesics has resulted in serious withdrawal symptoms, uncontrolled pain, and suicide. (2.5, 5.17)

3 DOSAGE FORMS AND STRENGTHS

Buccal film available in 75 mcg, 150 mcg, 300 mcg, 450 mcg, 600 mcg, 750 mcg, and 900 mcg dosage strengths. (3)

4 CONTRAINDICATIONS

- Significant respiratory depression (4)
- Acute or severe bronchial asthma in an unmonitored setting or in absence of resuscitative equipment (4)
- Known or suspected gastrointestinal obstruction, including paralytic ileus (4)
- Hypersensitivity to buprenorphine (4)

5 WARNINGS AND PRECAUTIONS

- Opioid-Induced Hyperalgesia and Allodynia: Opioid-Induced Hyperalgesia (OIH) occurs when an opioid analgesic paradoxically causes an increase in pain, or an increase in sensitivity to pain. If OIH is suspected, carefully consider appropriately decreasing the dose of the current opioid analgesic, or opioid rotation. (5.6).
- Life-Threatening Respiratory Depression in Patients with Chronic Pulmonary Disease or in Elderly, Cachectic, or Debilitated Patients: Regularly evaluate, particularly during initiation and titration. (5.7)
- Adrenal Insufficiency: If diagnosed, treat with physiologic replacement of corticosteroids, and wean patient off of the opioid. (5.8)
- Severe Hypotension: Regularly evaluate during dose initiation and titration. Avoid use of BELBUCA in patients with circulatory shock. (5.9)
- Risks of Use in Patients with Increased Intracranial Pressure, Brain Tumors, Head Injury, or Impaired Consciousness: Monitor for sedation and respiratory depression. Avoid use of BELBUCA in patients with impaired consciousness or coma. (5.10)

6 ADVERSE REACTIONS

Most common adverse reactions (>5%) include nausea, constipation, headache, vomiting, dizziness, and somnolence. (6.1)

To report SUSPECTED ADVERSE REACTIONS, contact Collegium Pharmaceutical, Inc. at 1-855-331-5615 or FDA at 1-800-FDA-1088 or www.fda.gov/medwatch.

7 DRUG INTERACTIONS

- Benzodiazepines: May increase buprenorphine-induced respiratory depression. Regularly evaluate patients on concurrent therapy closely. (7)
- CYP3A4 Inhibitors/Inducers: Initiating CYP3A4 inhibitors or discontinuing CYP3A4 inducers may result in an increase in buprenorphine plasma concentrations. Evaluate patients starting CYP3A4 inhibitors or stopping CYP3A4 inducers at frequent intervals for respiratory depression. (7)
- Serotonergic Drugs: Concomitant use may result in serotonin syndrome. Discontinue BELBUCA if serotonin syndrome is suspected. (7)
- Mixed Agonist/Antagonist and Partial Agonist Opioid Analgesics: Avoid use with BELBUCA because they may reduce analgesic effect of BELBUCA or precipitate withdrawal symptoms. (7)
- Monoamine Oxidase Inhibitors (MAOIs): Can potentiate the effects of buprenorphine. Avoid concomitant use in patients receiving MAOIs or within 14 days of stopping treatment with an MAOI. (7)

8 USE IN SPECIFIC POPULATIONS

- Pregnancy: May cause fetal harm. (8.1)
- Lactation: Not recommended. (8.2)
- Moderate or Severe Hepatic Impairment: Periodically assess for signs and symptoms of toxicity or overdose. (5.19, 8.6)

FULL PRESCRIBING INFORMATION

WARNING: SERIOUS AND LIFE-THREATENING RISKS FROM USE OF BELBUCA

Addiction, Abuse, and Misuse

Because the use of BELBUCA exposes patients and other users to the risks of opioid addiction, abuse, and misuse, which can lead to overdose and death, assess each patient's risk prior to prescribing and reassess all patients regularly for the development of these behaviors and conditions [see Warnings and Precautions (5.1)].

Life-Threatening Respiratory Depression

Serious, life-threatening, or fatal respiratory depression may occur with use of BELBUCA, especially during initiation or following a dosage increase. To reduce the risk of respiratory depression, proper dosing and titration of BELBUCA are essential. Misuse or abuse of BELBUCA by chewing, swallowing, snorting, or injecting buprenorphine extracted from the buccal film will result in the uncontrolled delivery of buprenorphine and pose a significant risk of overdose and death [see Dosage and Administration (2.1, 2.8), Warnings and Precautions (5.2)].

Accidental Exposure

Accidental exposure of even one dose of BELBUCA, especially in children, can result in a fatal overdose of buprenorphine [see Warnings and Precautions (5.2)].

Risks From Concomitant Use With Benzodiazepines Or Other CNS Depressants

Concomitant use of opioids with benzodiazepines or other central nervous system (CNS) depressants, including alcohol, may result in profound sedation, respiratory depression, coma, and death. Reserve concomitant prescribing of BELBUCA and benzodiazepines or other CNS depressants for use in patients for whom alternative treatment options are inadequate [see Warnings and Precautions (5.3), Drug Interactions (7)].

Neonatal Opioid Withdrawal Syndrome (NOWS)

Advise pregnant women using opioids for an extended period of time of the risk of Neonatal Opioid Withdrawal Syndrome, which may be life-threatening if not recognized and treated. Ensure that management by neonatology experts will be available at delivery [see Warnings and Precautions (5.4)].

Opioid Analgesic Risk Evaluation and Mitigation Strategy (REMS)

Healthcare providers are strongly encouraged to complete a REMS-compliant education program and to counsel patients and caregivers on serious risks, safe use, and the importance of reading the Medication Guide with each prescription [see Warnings and Precautions (5.5)].

1 INDICATIONS AND USAGE

BELBUCA is indicated for the management of severe and persistent pain that requires an opioid analgesic and that cannot be adequately treated with alternative options, including immediate-release opioids.

Limitations of Use

- Because of the risks of addiction, abuse, misuse, overdose, and death, which can occur at any dosage or duration and persist over the course of therapy [see Warnings and Precautions (5.1)], reserve opioid analgesics, including BELBUCA, for use in patients for whom alternative treatment options are ineffective, not tolerated, or would be otherwise inadequate to provide sufficient management of pain.
- BELBUCA is not indicated as an as-needed (prn) analgesic.

2 DOSAGE AND ADMINISTRATION

2.1 Important Dosage and Administration Instructions

- BELBUCA should be prescribed only by healthcare professionals who are knowledgeable about the use of extended-release/long-acting opioids and how to mitigate the associated risks.
- Use the lowest effective dosage for the shortest duration of time consistent with individual patient treatment goals [see Warnings and Precautions (5)]. Because the risk of overdose increases as opioid doses increase, reserve titration to higher doses of BELBUCA for patients in whom lower doses are insufficiently effective and in whom the expected benefits of using a higher dose opioid clearly outweigh the substantial risks.
- Initiate the dosing regimen for each patient individually, taking into account the patient's underlying cause and severity of pain, prior analgesic treatment and response, and risk factors for addiction, abuse, and misuse [see Warnings and Precautions (5.1)].
- Respiratory depression can occur at any time during opioid therapy, especially when initiating and following dosage increases with BELBUCA. Consider this risk when selecting an initial dose and when making dose adjustments [see Warnings and Precautions (5.2)].
- BELBUCA buccal film is for oral buccal use only and is to be applied to the buccal mucosa once daily or every 12 hours.
- Instruct patients not to use BELBUCA if the pouch seal is broken or the buccal film is cut, damaged, or changed in any way and to avoid applying BELBUCA to areas of the mouth with any open sores or lesions.

2.2 Patient Access to an Opioid Overdose Reversal Agent for the Emergency Treatment of Opioid Overdose

Inform patients and caregivers about opioid overdose reversal agents (e.g., naloxone, nalmefene). Discuss the importance of having access to an opioid overdose reversal agent, especially if the patient has risk factors for overdose (e.g., concomitant use of CNS depressants, a history of opioid use disorder, or prior opioid overdose) or if there are household members (including children) or other close contacts at risk for accidental ingestion or opioid overdose. The presence of risk factors for overdose should not prevent the management of pain in any patient [see Warnings and Precautions (5.1, 5.2, 5.3)].

Discuss the options for obtaining an opioid overdose reversal agent (e.g., prescription, over-the-counter, or as part of a community-based program) [see Warnings and Precautions (5.2)].

There are important differences among the opioid overdose reversal agents, such as route of administration, product strength, approved patient age range, and pharmacokinetics. Be familiar with these differences, as outlined in the approved labeling for those products, prior to recommending or prescribing such an agent.

2.3 Initial Dosage

It is safer to underestimate a patient's 24-hour oral buprenorphine dosage and provide rescue medication (e.g., immediate-release opioid) than to overestimate the 24-hour buprenorphine dosage and manage an adverse reaction due to an overdose. While useful tables of opioid equivalents are readily available, there is inter-patient variability in the potency of opioid drugs and opioid formulations. Frequently reevaluate patients for signs and symptoms of opioid withdrawal and for signs of oversedation/toxicity after converting patients to BELBUCA.

Use of BELBUCA in Patients who are not Opioid Tolerant

Initiate treatment in patients who are not opioid tolerant with a 75 mcg film once daily or, if tolerated, every 12 hours (see Table 1) for at least 4 days, then increase dose to 150 mcg every 12 hours. Individual titration to a dose that provides adequate analgesia and minimizes adverse reactions should proceed in increments of 150 mcg every 12 hours, no more frequently than every 4 days. Doses up to 450 mcg every 12 hours were studied in patients who were not opioid tolerant in the clinical trials [see Clinical Studies (14)].

Use of higher starting doses in patients who are not opioid tolerant may cause fatal respiratory depression [see Warnings and Precautions (5.2)].

Conversion from Other Opioid Analgesics to BELBUCA

- When BELBUCA therapy is initiated, discontinue all other opioid analgesics other than those used on an as needed basis for breakthrough pain when appropriate.
- There is a potential for buprenorphine to precipitate withdrawal in patients who are already on opioids. To reduce the risk of opioid withdrawal, taper patients to no more than 30 mg oral morphine sulfate equivalents (MSE) daily before beginning BELBUCA. Following analgesic taper, base the starting dose on the patient's daily opioid dose prior to taper, as described in Table 1. Patients may require additional short-acting analgesics during the taper period and during titration.
- BELBUCA may not provide adequate analgesia for patients requiring greater than 160 mg oral MSE per day. Consider the use of an alternate analgesic.
- There is inter-patient variability in the relative potency of opioid drugs and opioid formulations. Therefore, a conservative approach is advised when determining the total daily dosage of BELBUCA.

In a BELBUCA clinical trial with an open-label titration period, patients were converted from their prior opioid to BELBUCA using Table 1 as a guide for the initial BELBUCA dose.

Table 1: Initial BELBUCA Dose Based on Prior Opioid Expressed as Oral Morphine Sulfate Equivalents
Prior Daily Dose of Opioid Analgesic Before Taper to 30 mg Oral MSE | Initial BELBUCA Dose
Less than 30 mg oral MSE | BELBUCA 75 mcg once daily or every 12 hours
30 mg to 89 mg oral MSE | BELBUCA 150 mcg every 12 hours
90 mg to 160 mg oral MSE | BELBUCA 300 mcg every 12 hours
Greater than 160 mg oral MSE | Consider alternate analgesic

BELBUCA doses of 600 mcg, 750 mcg, and 900 mcg are only for use following titration from lower doses of BELBUCA. Individual titration should proceed in increments of 150 mcg every 12 hours, no more frequently than every 4 days.

Conversion from Methadone to BELBUCA

Regular evaluation is of particular importance when converting from methadone to other opioid agonists, including BELBUCA. The ratio between methadone and other opioid agonists may vary widely as a function of previous dose exposure. Methadone has a long half-life and can accumulate in the plasma.

2.4 Titration and Maintenance of Therapy

Individually titrate BELBUCA to a dose that provides adequate analgesia and minimizes adverse reactions. Continually reevaluate patients receiving BELBUCA to assess the maintenance of pain control, signs and symptoms of opioid withdrawal, and other adverse reactions, as well as to reassess for the development of addiction, abuse, or misuse [see Warnings and Precautions (5.1, 5.17)]. Frequent communication is important among the prescriber, other members of the healthcare team, the patient, and the caregiver/family during periods of changing analgesic requirements, including initial titration. During use of opioid therapy for an extended period of time, periodically reassess the continued need for opioid analgesics.

Patients who experience breakthrough pain may require dosage adjustment of BELBUCA or may need rescue medication with an appropriate dose of an immediate-release analgesic. If the level of pain increases after dose stabilization, attempt to identify the source of increased pain before increasing the BELBUCA dose. If after increasing the dosage, unacceptable opioid-related adverse reactions are observed (including an increase in pain after a dosage increase), consider reducing the dosage [see Warnings and Precautions (5)]. Adjust the dosage to obtain an appropriate balance between management of pain and opioid-related adverse reactions.

The minimum titration interval of BELBUCA is 4 days, based on the pharmacokinetic profile and time to reach steady-state plasma levels [see Clinical Pharmacology (12.3)]. Individual titration should proceed in increments of no more than 150 mcg every 12 hours.

The maximum BELBUCA dose is 900 mcg every 12 hours. Do not exceed a dose of BELBUCA 900 mcg every 12 hours due to the potential for QTc interval prolongation [see Warnings and Precautions (5.15), Adverse Reactions (6.1), Clinical Pharmacology (12.2)]. If pain is not adequately managed on BELBUCA 900 mcg, consider an alternate analgesic.

2.5 Safe Reduction or Discontinuation of BELBUCA

Do not rapidly reduce or abruptly discontinue BELBUCA in patients who may be physically dependent on opioids. Rapid reduction or abrupt discontinuation of opioid analgesics in patients who are physically dependent on opioids has resulted in serious withdrawal symptoms, uncontrolled pain, and suicide. Rapid reduction or abrupt discontinuation has also been associated with attempts to find other sources of opioid analgesics, which may be confused with drug-seeking for abuse. Patients may also attempt to treat their pain or withdrawal symptoms with illicit opioids, such as heroin, and other substances.

When a decision has been made to decrease the dose or discontinue therapy in an opioid-dependent patient taking BELBUCA, there are a variety of factors that should be considered, including the total daily dose of opioid (including BELBUCA) the patient has been taking, the duration of treatment, the type of pain being treated, and the physical and psychological attributes of the patient. It is important to ensure ongoing care of the patient and to agree on an appropriate tapering schedule and follow-up plan so that patient and provider goals and expectations are clear and realistic. When opioid analgesics are being discontinued due to a suspected substance use disorder, evaluate and treat the patient, or refer for evaluation and treatment of the substance use disorder. Treatment should include evidence-based approaches, such as medication-assisted treatment of opioid use disorder. Complex patients with comorbid pain and substance use disorders may benefit from referral to a specialist.

There are no standard opioid tapering schedules that are suitable for all patients. Good clinical practice dictates a patient-specific plan to taper the dose of the opioid gradually. For patients on BELBUCA who are physically opioid-dependent, initiate the taper by a small enough increment (e.g., no greater than 10% to 25% of the total daily dose) to avoid withdrawal symptoms, and proceed with dose-lowering at an interval of every 2 to 4 weeks. Patients who have been taking opioids for briefer periods of time may tolerate a more rapid taper.

It may be necessary to provide the patient with lower dosage strengths to accomplish a successful taper. Reassess the patient frequently to manage pain and withdrawal symptoms, should they emerge. Common withdrawal symptoms include restlessness, lacrimation, rhinorrhea, yawning, perspiration, chills, myalgia, and mydriasis. Other signs and symptoms also may develop, including irritability, anxiety, backache, joint pain, weakness, abdominal cramps, insomnia, nausea, anorexia, vomiting, diarrhea, or increased blood pressure, respiratory rate, or heart rate. If withdrawal symptoms arise, it may be necessary to pause the taper for a period of time or raise the dose of the opioid analgesic to the previous dose, and then proceed with a slower taper. In addition, evaluate patients for any changes in mood, emergence of suicidal thoughts, or use of other substances.

When managing patients taking opioid analgesics, particularly those who have been treated for an extended period of time and/or with high doses for chronic pain, ensure that a multimodal approach to pain management, including mental health support (if needed), is in place prior to initiating an opioid analgesic taper. A multimodal approach to pain management may optimize the treatment of chronic pain, as well as assist with the successful tapering of the opioid analgesic [see Warnings and Precautions (5.17), Drug Abuse and Dependence (9.3)].

2.6 Dosage Modifications in Patients with Severe Hepatic Impairment

In patients with severe hepatic impairment (i.e., Child-Pugh C), reduce the starting dose and reduce the titration dose by half that of patients with normal liver function, from 150 mcg to 75 mcg [see Warnings and Precautions (5.19), Use in Special Populations (8.6), Clinical Pharmacology (12.3)].

2.7 Dosage Modifications in Patients with Oral Mucositis

In patients with known or suspected mucositis, reduce the starting dosage and titration incremental dosage by half compared to patients without mucositis [see Warnings and Precautions (5.20), Clinical Pharmacology (12.3)].

2.8 Administration of BELBUCA

BELBUCA should not be used if the package seal is broken or the film is cut, damaged, or changed in any way.

First, the patient must use the tongue to wet the inside of the cheek or rinse the mouth with water to wet the area for placement of BELBUCA. BELBUCA is then applied immediately after removal from the individually sealed package. The yellow side of the BELBUCA film is placed against the inside of the cheek. The entire BELBUCA film is held in place with clean, dry fingers for 5 seconds and then left in place on the inside of the cheek until fully dissolved.

BELBUCA adheres to the moist buccal mucosa and will completely dissolve after application, usually within 30 minutes. The film should not be manipulated with the tongue or finger(s) and eating food and drinking liquids should be avoided until the film has dissolved.

Advise patients to do the following after the product has completely dissolved in the oral mucosa: take a sip of water, swish gently around the teeth and gums, and swallow. Advise patients to wait for at least one hour after taking BELBUCA before brushing teeth [see Warnings and Precautions (5.14), Adverse Reactions (6.2)].

A BELBUCA film, if chewed or swallowed, may result in lower peak concentrations and lower bioavailability than when used as directed.

Demonstrate proper administration technique to the patient.

3 DOSAGE FORMS AND STRENGTHS

Dosage strengths of BELBUCA are based on the active moiety, buprenorphine.

The 75 mcg dosage form is a buccal film that contains 75 mcg buprenorphine. The film is white on one side, with E0 printed in black, and yellow on the other side.

The 150 mcg dosage form is a buccal film that contains 150 mcg buprenorphine. The film is white on one side, with E1 printed in black, and yellow on the other side.

The 300 mcg dosage form is a buccal film that contains 300 mcg buprenorphine. The film is white on one side, with E3 printed in black, and yellow on the other side.

The 450 mcg dosage form is a buccal film that contains 450 mcg buprenorphine. The film is white on one side, with E4 printed in black, and yellow on the other side.

The 600 mcg dosage form is a buccal film that contains 600 mcg buprenorphine. The film is white on one side, with E6 printed in black, and yellow on the other side.

The 750 mcg dosage form is a buccal film that contains 750 mcg buprenorphine. The film is white on one side, with E7 printed in black, and yellow on the other side.

The 900 mcg dosage form is a buccal film that contains 900 mcg buprenorphine. The film is white on one side, with E9 printed in black, and yellow on the other side.

4 CONTRAINDICATIONS

BELBUCA is contraindicated in patients with:

- Significant respiratory depression [see Warnings and Precautions (5.2)]
- Acute or severe bronchial asthma in an unmonitored setting or in the absence of resuscitative equipment [see Warnings and Precautions (5.7)]
- Known or suspected gastrointestinal obstruction, including paralytic ileus [see Warnings and Precautions (5.12)]
- Hypersensitivity (e.g., anaphylaxis) to buprenorphine [see Warnings and Precautions (5.16), Adverse Reactions (6)]

5 WARNINGS AND PRECAUTIONS

5.1 Addiction, Abuse, and Misuse

BELBUCA contains buprenorphine, a Schedule III controlled substance. As an opioid, BELBUCA exposes users to the risks of addiction, abuse, and misuse [see Drug Abuse and Dependence (9)].

Although the risk of addiction in any individual is unknown, it can occur in patients appropriately prescribed BELBUCA. Addiction can occur at recommended dosages and if the drug is misused or abused. The risk of opioid-related overdose or overdose-related death is increased with higher opioid doses, and this risk persists over the course of therapy. In postmarketing studies, addiction, abuse, misuse, and fatal and non-fatal opioid overdose were observed in patients with long-term opioid use [see Adverse Reactions (6.2)].

Assess each patient's risk for opioid addiction, abuse, or misuse prior to prescribing BELBUCA and reassess all patients receiving BELBUCA for the development of these behaviors and conditions. Risks are increased in patients with a personal or family history of substance abuse (including drug or alcohol abuse or addiction) or mental illness (e.g., major depression). The potential for these risks should not, however, prevent the proper management of pain in any given patient. Patients at increased risk may be prescribed opioids such as BELBUCA but use in such patients necessitates intensive counseling about the risks and proper use of BELBUCA, along with frequent reevaluation for signs of addiction, abuse, or misuse. Consider recommending or prescribing an opioid overdose reversal agent [see Dosage and Administration (2.2), Warnings and Precautions (5.2)].

Abuse or misuse of BELBUCA by swallowing may cause choking, overdose, and death [see Overdosage (10)].

Opioids are sought for nonmedical use and are subject to diversion from legitimate prescribed use. Consider these risks when prescribing or dispensing BELBUCA. Strategies to reduce the risk include prescribing the drug in the smallest appropriate quantity and advising the patient on careful storage of the drug during the course of treatment and the proper disposal of unused drug. Contact local state professional licensing board or state-controlled substances authority for information on how to prevent and detect abuse or diversion of this product.

5.2 Life-Threatening Respiratory Depression

Serious, life-threatening, or fatal respiratory depression has been reported with the use of opioids, even when used as recommended. Respiratory depression, if not immediately recognized and treated, may lead to respiratory arrest and death. Management of respiratory depression may include close observation, supportive measures, and use of opioid overdose reversal agents, depending on the patient's clinical status [see Overdosage (10)]. Carbon dioxide (CO2) retention from opioid-induced respiratory depression can exacerbate the sedating effects of opioids.

While serious, life-threatening or fatal respiratory depression can occur at any time during the use of BELBUCA, the risk is greatest during initiation of therapy or following a dosage increase.

To reduce the risk of respiratory depression, proper dosing and titration of BELBUCA are essential [see Dosage and Administration (2)]. Overestimating the dose of BELBUCA when converting patients from another opioid product may result in fatal overdose with the first dose.

Accidental exposure to BELBUCA, especially in children, can result in respiratory depression and death due to an overdose of buprenorphine.

Educate patients and caregivers on how to recognize respiratory depression and emphasize the importance of calling 911 or getting emergency medical help right away in the event of a known or suspected overdose.

Opioids can cause sleep-related breathing disorders including central sleep apnea (CSA) and sleep-related hypoxemia. Opioid use increases the risk of CSA in a dose-dependent fashion. In patients who present with CSA, consider decreasing the opioid dosage using best practices for opioid taper [see Dosage and Administration (2.5)].

Patient Access to an Opioid Overdose Reversal Agent for the Emergency Treatment of Opioid Overdose

Inform patients and caregivers about opioid overdose reversal agents (e.g., naloxone, nalmefene). Discuss the importance of having access to an opioid overdose reversal agent, especially if the patient has risk factors for overdose (e.g., concomitant use of CNS depressants, a history of opioid use disorder, or prior opioid overdose) or if there are household members (including children) or other close contacts at risk for accidental ingestion or opioid overdose. The presence of risk factors for overdose should not prevent the management of pain in any patient [see Warnings and Precautions (5.1, 5.3)].

Discuss the options for obtaining an opioid overdose reversal agent (e.g., prescription, over-the-counter, or as part of a community-based program).

There are important differences among the opioid overdose reversal agents, such as route of administration, product strength, approved patient age range, and pharmacokinetics. Be familiar with these differences, as outlined in the approved labeling for those products, prior to recommending or prescribing such an agent.

Educate patients and caregivers on how to recognize respiratory depression, and how to use an opioid overdose reversal agent for the emergency treatment of opioid overdose. Emphasize the importance of calling 911 or getting emergency medical help, even if an opioid overdose reversal agent is administered [see Dosage and Administration (2.2), Warnings and Precautions (5.1, 5.3), Overdosage (10)].

5.3 Risks from Concomitant Use with Benzodiazepines or Other CNS Depressants

Profound sedation, respiratory depression, coma, and death may result from the concomitant use of BELBUCA with benzodiazepines and/or other CNS depressants, including alcohol (e.g., non-benzodiazepine sedatives/hypnotics, anxiolytics, tranquilizers, muscle relaxants, general anesthetics, antipsychotics, gabapentinoids [gabapentin or pregabalin], and other opioids). Because of these risks, reserve concomitant prescribing of these drugs for use in patients for whom alternative treatment options are inadequate.

Observational studies have demonstrated that concomitant use of opioid analgesics and benzodiazepines increases the risk of drug-related mortality compared to use of opioid analgesics alone. Because of similar pharmacological properties, it is reasonable to expect similar risk with the concomitant use of other CNS depressant drugs with opioid analgesics [see Drug Interactions (7)].

If the decision is made to prescribe a benzodiazepine or other CNS depressant concomitantly with an opioid analgesic, prescribe the lowest effective dosages and minimum durations of concomitant use. In patients already receiving an opioid analgesic, prescribe a lower initial dose of the benzodiazepine or other CNS depressant than indicated in the absence of an opioid, and titrate based on clinical response. If an opioid analgesic is initiated in a patient already taking a benzodiazepine or other CNS depressant, prescribe a lower initial dose of the opioid analgesic, and titrate based on clinical response. Inform patients and caregivers of this potential interaction and educate them on signs and symptoms of respiratory depression (including sedation).

If concomitant use is warranted, consider recommending or prescribing an opioid overdose reversal agent [see Dosage and Administration (2.2), Warnings and Precautions (5.2), Overdosage (10)]. Advise both patients and caregivers about the risks of respiratory depression and sedation when BELBUCA is used with benzodiazepines or other CNS depressants (including alcohol and illicit drugs). Advise patients not to drive or operate heavy machinery until the effects of concomitant use of the benzodiazepine or other CNS depressant have been determined. Screen patients for risk of substance use disorders, including opioid abuse and misuse, and warn them of the risk for overdose and death associated with the use of additional CNS depressants including alcohol and illicit drugs [see Drug Interactions (7)].

5.4 Neonatal Opioid Withdrawal Syndrome

Use of BELBUCA for an extended period of time during pregnancy can result in withdrawal in the neonate. Neonatal opioid withdrawal syndrome, unlike opioid withdrawal syndrome in adults, may be life-threatening if not recognized and treated, and requires management according to protocols developed by neonatology experts. Observe newborns for signs of neonatal opioid withdrawal syndrome and manage accordingly. Advise pregnant women using opioids for an extended period of time of the risk of neonatal opioid withdrawal syndrome and ensure that appropriate treatment will be available [see Use in Specific Populations (8.1)].

5.5 Opioid Analgesic Risk Evaluation and Mitigation Strategy (REMS)

To ensure that the benefits of opioid analgesics outweigh the risks of addiction, abuse, and misuse, the Food and Drug Administration (FDA) has required a Risk Evaluation and Mitigation Strategy (REMS) for these products. Under the requirements of the REMS, drug companies with approved opioid analgesic products must make REMS-compliant education programs available to healthcare providers. Healthcare providers are strongly encouraged to do all of the following:

- Complete a REMS-compliant education program offered by an accredited provider of continuing education (CE) or another education program that includes all the elements of the FDA Education Blueprint for Health Care Providers Involved in the Management or Support of Patients with Pain.
- Discuss the safe use, serious risks, and proper storage and disposal of opioid analgesics with patients and/or their caregivers every time these medicines are prescribed. The Patient Counseling Guide (PCG) can be obtained at this link: www.fda.gov/OpioidAnalgesicREMSPCG.
- Emphasize to patients and their caregivers the importance of reading the Medication Guide that they will receive from their pharmacist every time an opioid analgesic is dispensed to them.
- Consider using other tools to improve patient, household, and community safety, such as patient-prescriber agreements that reinforce patient-prescriber responsibilities.

To obtain further information on the opioid analgesic REMS and for a list of accredited REMS CME/CE, call 1-800-503-0784, or log on to www.opioidanalgesicrems.com. The FDA Blueprint can be found at www.fda.gov/OpioidAnalgesicREMSBlueprint.

5.6 Opioid-Induced Hyperalgesia and Allodynia

Opioid-Induced Hyperalgesia (OIH) occurs when an opioid analgesic paradoxically causes an increase in pain, or an increase in sensitivity to pain. This condition differs from tolerance, which is the need for increasing doses of opioids to maintain a defined effect [see Dependence (9.3)]. Symptoms of OIH include (but may not be limited to) increased levels of pain upon opioid dosage increase, decreased levels of pain upon opioid dosage decrease, or pain from ordinarily non-painful stimuli (allodynia). These symptoms may suggest OIH only if there is no evidence of underlying disease progression, opioid tolerance, opioid withdrawal, or addictive behavior.

Cases of OIH have been reported, both with short-term and longer-term use of opioid analgesics. Though the mechanism of OIH is not fully understood, multiple biochemical pathways have been implicated. Medical literature suggests a strong biologic plausibility between opioid analgesics and OIH and allodynia. If a patient is suspected to be experiencing OIH, carefully consider appropriately decreasing the dose of the current opioid analgesic or opioid rotation (safely switching the patient to a different opioid moiety) [see Dosage and Administration (2.5), Warnings and Precautions (5.17)].

5.7 Life-Threatening Respiratory Depression in Patients with Chronic Pulmonary Disease or in Elderly, Cachectic, or Debilitated Patients

The use of BELBUCA in patients with acute or severe bronchial asthma in an unmonitored setting or in the absence of resuscitative equipment is contraindicated.

Patients with Chronic Pulmonary Disease: BELBUCA-treated patients with significant chronic obstructive pulmonary disease or cor pulmonale, and those with substantially decreased respiratory reserve, hypoxia, hypercapnia, or pre-existing respiratory depression are at increased risk of decreased respiratory drive, including apnea, even at recommended dosages of BELBUCA [see Warnings and Precautions (5.2)].

Elderly, Cachectic, or Debilitated Patients: Life-threatening respiratory depression is more likely to occur in elderly, cachectic, or debilitated patients as they may have altered pharmacokinetics or altered clearance compared to younger, healthier patients [see Warnings and Precautions (5.2)].

Regularly evaluate patients, particularly when initiating and titrating BELBUCA and when BELBUCA is given concomitantly with other drugs that depress respiration [see Warnings and Precautions (5.2, 5.3), Drug Interactions (7)]. Alternatively, consider the use of non-opioid analgesics in these patients.

5.8 Adrenal Insufficiency

Cases of adrenal insufficiency have been reported with opioid use, more often following greater than one month of use. Presentation of adrenal insufficiency may include non-specific symptoms and signs including nausea, vomiting, anorexia, fatigue, weakness, dizziness, and low blood pressure. If adrenal insufficiency is suspected, confirm the diagnosis with diagnostic testing as soon as possible. If adrenal insufficiency is diagnosed, treat with physiologic replacement doses of corticosteroids. Wean the patient off of the opioid to allow adrenal function to recover and continue corticosteroid treatment until adrenal function recovers. Other opioids may be tried as some cases reported use of a different opioid without recurrence of adrenal insufficiency. The information available does not identify any particular opioids as being more likely to be associated with adrenal insufficiency.

5.9 Severe Hypotension

BELBUCA may cause severe hypotension including orthostatic hypotension and syncope in ambulatory patients. There is an increased risk in patients whose ability to maintain blood pressure has already been compromised by a reduced blood volume or concurrent administration of certain CNS depressant drugs (e.g., phenothiazines or general anesthetics) [see Drug Interactions (7)]. Regularly evaluate these patients for signs of hypotension after initiating or titrating the dosage of BELBUCA. In patients with circulatory shock, BELBUCA may cause vasodilation that can further reduce cardiac output and blood pressure. Avoid the use of BELBUCA in patients with circulatory shock.

5.10 Risks of Use in Patients with Increased Intracranial Pressure, Brain Tumors, Head Injury, or Impaired Consciousness

In patients who may be susceptible to the intracranial effects of CO2 retention (e.g., those with evidence of increased intracranial pressure or brain tumors), BELBUCA may reduce respiratory drive, and the resultant CO2 retention can further increase intracranial pressure. Monitor such patients for signs of sedation and respiratory depression, particularly when initiating therapy with BELBUCA.

Opioids may also obscure the clinical course in a patient with a head injury. Avoid the use of BELBUCA in patients with impaired consciousness or coma.

5.11 Hepatotoxicity

Cases of cytolytic hepatitis and hepatitis with jaundice have been observed in individuals receiving sublingual formulations of buprenorphine for the treatment of opioid dependence, both in clinical trials and in postmarketing adverse event reports. The spectrum of abnormalities ranges from transient asymptomatic elevations in hepatic transaminases to case reports of hepatic failure, hepatic necrosis, hepatorenal syndrome, and hepatic encephalopathy. In many cases, the presence of pre-existing liver enzyme abnormalities, infection with hepatitis B or hepatitis C virus, concomitant usage of other potentially hepatotoxic drugs, and ongoing injection drug abuse may have played a causative or contributory role. For patients at increased risk of hepatotoxicity (e.g., patients with a history of excessive alcohol intake, intravenous drug abuse or liver disease), obtain baseline liver enzyme levels and periodically reassess during treatment with BELBUCA.

5.12 Risk of Gastrointestinal Complications

BELBUCA is contraindicated in patients with known or suspected gastrointestinal obstruction, including paralytic ileus.

BELBUCA may cause spasm of the sphincter of Oddi. Opioids may cause increases in the serum amylase. Regularly evaluate patients with biliary tract disease, including acute pancreatitis, for worsening symptoms.

Cases of opioid-induced esophageal dysfunction (OIED) have been reported in patients taking opioids. The risk of OIED may increase as the dose and/or duration of opioids increases. Regularly evaluate patients for signs and symptoms of OIED (e.g., dysphagia, regurgitation, non-cardiac chest pain) and, if necessary, adjust opioid therapy as clinically appropriate [see Clinical Pharmacology (12.2)].

5.13 Increased Risk of Seizures in Patients with Seizure Disorders

The buprenorphine in BELBUCA may increase the frequency of seizures in patients with seizure disorders and may increase the risk of seizures occurring in other clinical settings associated with seizures. Regularly evaluate patients with a history of seizure disorders for worsened seizure control during BELBUCA therapy.

5.14 Dental Adverse Events

Cases of dental caries, some severe (i.e., tooth fracture, tooth loss), have been reported following the use of transmucosal buprenorphine-containing products. Reported events include cavities, tooth decay, dental abscesses/infection, rampant caries, tooth erosion, fillings falling out, and, in some cases, total tooth loss. Treatment for these events included tooth extraction, root canal, dental surgery, as well as other restorative procedures (i.e., fillings, crowns, implants, dentures). Multiple cases were reported in individuals without any prior history of dental problems.

Refer patients to dental care services and encourage them to have regular dental checkups while taking BELBUCA. Educate patients to seek dental care and strategies to maintain or improve oral health while being treated with transmucosal buprenorphine-containing products. Strategies include, but are not limited to, gently rinsing the teeth and gums with water and then swallowing after BELBUCA has been completely dissolved in the oral mucosa. Advise patients to wait for at least one hour after taking BELBUCA before brushing teeth [see Dosing and Administration (2.8)].

5.15 QTc Prolongation

Thorough QT studies with buprenorphine products have demonstrated QT prolongation ≤15 msec. This QTc prolongation effect does not appear to be mediated by hERG channels. Based on these two findings, buprenorphine is unlikely to be pro-arrhythmic when used alone in patients without risk factors. The risk of combining buprenorphine with other QT-prolonging agents is not known.

Consider these observations in clinical decisions when prescribing BELBUCA to patients with risk factors such as hypokalemia, bradycardia, recent conversion from atrial fibrillation, congestive heart failure, digitalis therapy, baseline QT prolongation, subclinical long-QT syndrome, or severe hypomagnesemia [see Dosage and Administration (2.4), Adverse Reactions (6.1), Clinical Pharmacology (12.2)].

5.16 Anaphylactic/Allergic Reactions

Cases of acute and chronic hypersensitivity to buprenorphine have been reported both in clinical trials and in post-marketing experience. The most common signs and symptoms include rashes, hives, and pruritus. Cases of bronchospasm, angioneurotic edema, and anaphylactic shock have been reported. BELBUCA is contraindicated in patients with a history of hypersensitivity to buprenorphine.

5.17 Withdrawal

Do not rapidly reduce or abruptly discontinue BELBUCA in a patient physically dependent on opioids. When discontinuing BELBUCA in a physically dependent patient, gradually taper the dosage. Rapid tapering of buprenorphine in a patient physically dependent on opioids may lead to a withdrawal syndrome and return of pain [see Dosage and Administration (2.5), Drug Abuse and Dependence (9.3)].

Additionally, the use of BELBUCA, a partial agonist opioid analgesic, in patients who are receiving a full opioid agonist analgesic may reduce the analgesic effect and/or precipitate withdrawal symptoms. Avoid concomitant use of BELBUCA with a full opioid agonist analgesic.

5.18 Risks of Driving and Operating Machinery

BELBUCA may impair the mental and physical abilities needed to perform potentially hazardous activities such as driving a car or operating machinery. Warn patients not to drive or operate dangerous machinery unless they are tolerant to side effects of BELBUCA and know how they will react to the medication.

5.19 Risk of Overdose in Patients with Moderate to Severe Hepatic Impairment

In a pharmacokinetic study in subjects dosed with buprenorphine sublingual tablets, buprenorphine plasma levels were found to be higher and the half-life was found to be longer in subjects with moderate and severe hepatic impairment, but not in subjects with mild hepatic impairment. For patients with severe hepatic impairment, a dose adjustment is recommended, and patients with moderate or severe hepatic impairment should be periodically assessed for signs and symptoms of toxicity or overdose caused by increased levels of buprenorphine [see Dosage and Administration (2.6), Use in Specific Populations (8.6)].

5.20 Risks of Use in Cancer Patients with Oral Mucositis

Cancer patients with oral mucositis may absorb buprenorphine more rapidly than intended and are likely to experience higher plasma levels of the opioid. For patients with known or suspected mucositis, a dose reduction is recommended. Regularly evaluate these patients for signs and symptoms of toxicity or overdose caused by increased levels of buprenorphine [see Dosage and Administration (2.7), Clinical Pharmacology (12.3)].

6 ADVERSE REACTIONS

The following serious adverse reactions described elsewhere in the labeling include:

- Addiction, Abuse, and Misuse [see Warnings and Precautions (5.1)]
- Life-Threatening Respiratory Depression [see Warnings and Precautions (5.2)]
- Interactions with Benzodiazepines and Other CNS Depressants [see Warnings and Precautions (5.3)]
- Neonatal Opioid Withdrawal Syndrome [see Warnings and Precautions (5.4)]
- Opioid-Induced Hyperalgesia and Allodynia [see Warnings and Precautions (5.6)]
- Adrenal Insufficiency [see Warnings and Precautions (5.8)]
- Severe Hypotension [see Warnings and Precautions (5.9)]
- Hepatotoxicity [see Warnings and Precautions (5.11)]
- Gastrointestinal Adverse Reactions [see Warnings and Precautions (5.12)]
- Seizures [see Warnings and Precautions (5.13)]
- QTc Prolongation [see Warnings and Precautions (5.15)]
- Anaphylactic/Allergic Reactions [see Warnings and Precautions (5.16)]

6.1 Clinical Trial Experience

Because clinical trials are conducted under widely varying conditions, adverse reaction rates observed in the clinical trials of a drug cannot be directly compared to rates in the clinical trials of another drug and may not reflect the rates observed in practice.

A total of 2,127 patients were treated with BELBUCA in controlled and open-label chronic pain trials. There were 504 patients treated for approximately six months and 253 patients treated for approximately one year. The clinical trial population consisted of patients with chronic moderate-to-severe pain.

The most common serious adverse drug reactions (all ≤ 0.2%) occurring during clinical trials with BELBUCA were: cellulitis, pneumonia, ileus, atrial fibrillation, coronary artery disease, cerebrovascular accident, syncope, transient ischemic attack, chest pain, non-cardiac chest pain, ankle fracture, cholecystitis, osteoarthritis, and dehydration.

The most common adverse events (≥ 2%) leading to discontinuation were nausea, vomiting, and liver function test abnormality.

The most common adverse events (≥ 5%) reported by patients who were not opioid tolerant, opioid-experienced patients, and overall patients exposed to BELBUCA in clinical trials and compared against placebo are shown in Table 2, Table 3 and Table 4:

Table 2: Adverse Events Reported in ≥ 5% of Patients during the Open-Label Titration Phase and Double-Blind Treatment Phase of Controlled Studies: Patients Who Were Not Opioid Tolerant
 | Open-Label Titration Phase | Double-Blind Treatment Phase
MedDRA Preferred Term | BELBUCA (N=749) | BELBUCA (N=229) | Placebo (N=232)
Nausea | 50% | 10% | 7%
Constipation | 13% | 4% | 3%
Vomiting | 8% | 4% | <1%
Headache | 8% | 2% | 3%
Dizziness | 6% | 2% | <1%
Somnolence | 7% | 1% | <1%
Fatigue | 5% | 0% | 1%

Table 3: Adverse Events Reported in ≥ 5% of Patients during the Open-Label Titration Phase and Double-Blind Treatment Phase of Controlled Studies: Opioid-Experienced Patients
 | Open-Label Titration Phase | Double-Blind Treatment Phase
MedDRA Preferred Term | BELBUCA (N=810) | BELBUCA (N=254) | Placebo (N=256)
Nausea | 17% | 7% | 7%
Constipation | 8% | 3% | 1%
Vomiting | 7% | 5% | 2%
Headache | 7% | 2% | 3%
Dizziness | 5% | 2% | <1%
Somnolence | 5% | 1% | <1%
Drug Withdrawal Syndrome | 0% | 4% | 10%

Table 4: Adverse Events Reported in ≥ 5% of Patients during the Open-Label Titration Phase and Double-Blind Treatment Phase of Controlled Studies
 | Open-Label Titration Phase | Double-Blind Treatment Phase
MedDRA Preferred Term | BELBUCA (N=1889) | BELBUCA (N=600) | Placebo (N=606)
Nausea | 33% | 9% | 8%
Constipation | 11% | 4% | 2%
Vomiting | 7% | 5% | 2%
Headache | 8% | 4% | 3%
Dizziness | 6% | 2% | <1%
Somnolence | 6% | <1% | <1%
Drug Withdrawal Syndrome | 1% | 2% | 5%

The most common (≥ 5%), common (≥ 1% to < 5%), and least common (< 1%) adverse reactions reported by patients taking BELBUCA in the controlled and open-label clinical studies are presented below:

Most common adverse reactions (≥ 5%): nausea, constipation, headache, vomiting, fatigue, dizziness, and somnolence.

Common (≥ 1% to < 5%) adverse reactions (organized by MedDRA [Medical Dictionary for Regulatory Activities] System Organ Class):

Blood and lymphatic system disorders: anemia

Gastrointestinal disorders: abdominal pain, diarrhea, dry mouth

General disorders and administration site conditions: peripheral edema, pyrexia, drug withdrawal syndrome

Infections and infestations: upper respiratory tract infection, urinary tract infection, nasopharyngitis, sinusitis, bronchitis, gastroenteritis

Injury, poisoning, and procedural complications: contusion, fall

Metabolism and nutrition disorders: decreased appetite

Musculoskeletal and connective tissue disorders: muscle spasms, back pain

Psychiatric disorders: anxiety, insomnia, depression

Respiratory, thoracic and mediastinal disorders: oropharyngeal pain, sinus congestion

Skin and subcutaneous tissue disorders: hyperhidrosis, pruritus, rash

Vascular disorders: hot flush, hypertension

Least common (<1%) adverse reactions:

Abdominal discomfort, acute sinusitis, dyspepsia, toothache, asthenia, chills, cellulitis, tooth abscess, excoriation, laceration, aspartate aminotransferase increased, blood pressure increased, blood testosterone decreased, electrocardiogram QT prolonged, liver function test abnormal, musculoskeletal pain, neck pain, hypoesthesia, lethargy, migraine, tremor, cough, dyspnea, nasal congestion, rhinorrhea.

6.2 Postmarketing Experience

The following adverse reactions have been identified during post approval use of buprenorphine. Because these reactions are reported voluntarily from a population of uncertain size, it is not always possible to reliably estimate their frequency or establish a causal relationship to drug exposure.

Serotonin syndrome: Cases of serotonin syndrome, a potentially life-threatening condition, have been reported during concomitant use of opioids with serotonergic drugs.

Adrenal insufficiency: Cases of adrenal insufficiency have been reported with opioid use, more often following greater than one month of use.

Anaphylaxis: Anaphylaxis has been reported with ingredients contained in BELBUCA.

Androgen deficiency: Cases of androgen deficiency have occurred with use of opioids for an extended period of time. [see Clinical Pharmacology (12.2)].

Hyperalgesia and Allodynia: Cases of hyperalgesia and allodynia have been reported with opioid therapy of any duration [see Warnings and Precautions (5.6)].

Local reactions: dental decay (including caries, tooth fracture, and tooth loss).

Hypoglycemia: Cases of hypoglycemia have been reported in patients taking opioids. Most reports were in patients with at least one predisposing risk factor (e.g., diabetes).

Opioid-induced esophageal dysfunction (OIED): Cases of OIED have been reported in patients taking opioids, and may occur more frequently in patients taking higher doses of opioids, and/or in patients taking opioids longer term [see Warnings and Precautions (5.12)].

Adverse Reactions from Observational Studies

A prospective, observational cohort study estimated the risks of addiction, abuse, and misuse in patients initiating long-term use of Schedule II opioid analgesics between 2017 and 2021. Study participants included in one or more analyses had been enrolled in selected insurance plans or health systems for at least one year, were free of at least one outcome at baseline, completed a minimum number of follow-up assessments, and either: 1) filled multiple extended-release/long-acting opioid analgesic prescriptions during a 90-day period (n=978); or 2) filled any Schedule II opioid analgesic prescriptions covering at least 70 of 90 days (n=1,244). Those included also had no dispensing of the qualifying opioids in the previous 6 months.

Over 12 months:

- approximately 1% to 6% of participants across the two cohorts newly met criteria for addiction, as assessed with two validated interview-based measures of moderate-to-severe opioid use disorder based on Diagnostic and Statistical Manual of Mental Disorders, Fifth Edition (DSM-5) criteria, and
- approximately 9% and 22% of participants across the two cohorts newly met criteria for prescription opioid abuse and misuse [defined in Drug Abuse and Dependence (9.2)], respectively, as measured with a validated self-reported instrument.

A retrospective, observational cohort study estimated the risk of opioid-involved overdose or opioid overdose-related death in patients with new long-term use of Schedule II opioid analgesics from 2006 through 2016 (n=220,249). Included patients had been enrolled in either one of two commercial insurance programs, one managed care program, or one Medicaid program for at least 9 months. New long-term use was defined as having Schedule II opioid analgesic prescriptions covering at least 70 days' supply over the 3 months prior to study entry and none during the preceding 6 months. Patients were excluded if they had an opioid-involved overdose in the 9 months prior to study entry. Overdose was measured using a validated medical code-based algorithm with linkage to the National Death Index database. The 5-year cumulative incidence estimates for opioid-involved overdose or opioid overdose-related death ranged from approximately 1.5% to 4% across study sites, counting only the first event during follow-up. Approximately 17% of first opioid overdoses observed over the entire study period (5-11 years, depending on the study site) were fatal. Higher baseline opioid dose was the strongest and most consistent predictor of opioid-involved overdose or opioid overdose-related death. Study exclusion criteria may have selected patients at lower risk of overdose, and substantial loss to follow-up (approximately 80%) also may have biased estimates.

The risk estimates from the studies described above may not be generalizable to all patients receiving opioid analgesics, such as those with exposures shorter or longer than the duration evaluated in the studies.

7 DRUG INTERACTIONS

Table 5 includes clinically significant drug interactions with BELBUCA.

Table 5: Clinically Significant Drug Interactions
Benzodiazepines
Clinical Impact: | There have been a number of reports regarding coma and death associated with the misuse and abuse of the combination of buprenorphine and benzodiazepines. In many, but not all of these cases, buprenorphine was misused by self-injection of crushed buprenorphine tablets. Preclinical studies have shown that the combination of benzodiazepines and buprenorphine altered the usual ceiling effect on buprenorphine-induced respiratory depression, making the respiratory effects of buprenorphine appear similar to those of full opioid agonists.
Intervention: | Regularly evaluate patients with concurrent use of BELBUCA and benzodiazepines. Warn patients that it is extremely dangerous to self-administer benzodiazepines while taking BELBUCA and warn patients to use benzodiazepines concurrently with BELBUCA only as directed by their physician.
Benzodiazepines and Other Central Nervous System (CNS) Depressants
Clinical Impact: | Due to additive pharmacologic effect, the concomitant use of benzodiazepines or other CNS depressants, including alcohol, can increase the risk of hypotension, respiratory depression, profound sedation, coma, and death [see Warnings and Precautions (5.3)].
Intervention: | Reserve concomitant prescribing of these drugs for use in patients for whom alternative treatment options are inadequate. Limit dosages and durations to the minimum required. Inform patients and caregivers of this potential interaction and educate them on the signs and symptoms of respiratory depression (including sedation). If concomitant use is warranted, consider recommending or prescribing an opioid overdose reversal agent [see Dosage and Administration (2.2), Warnings and Precautions (5.1, 5.2, 5.3)].
Examples: | Benzodiazepines and other sedatives/hypnotics, anxiolytics, tranquilizers, muscle relaxants, general anesthetics, antipsychotics, gabapentinoids (gabapentin or pregabalin),, other opioids, alcohol.
Inhibitors of CYP3A4
Clinical Impact: | The concomitant use of BELBUCA and CYP3A4 inhibitors can increase the plasma concentration of buprenorphine, resulting in increased or prolonged opioid effects, particularly when an inhibitor is added after a stable dose of BELBUCA is achieved. After stopping a CYP3A4 inhibitor, as the effects of the inhibitor decline, the buprenorphine plasma concentration will decrease [see Clinical Pharmacology (12.3)], potentially resulting in decreased opioid efficacy or a withdrawal syndrome in patients who had developed physical dependence to buprenorphine.
Intervention: | If concomitant use is necessary, consider dosage reduction of BELBUCA until stable drug effects are achieved. Evaluate patients at frequent intervals for respiratory depression and sedation. If a CYP3A4 inhibitor is discontinued, consider increasing the BELBUCA dosage until stable drug effects are achieved. Assess for signs of opioid withdrawal.
Examples: | Macrolide antibiotics (e.g., erythromycin), azole-antifungal agents (e.g., ketoconazole), protease inhibitors (e.g., ritonavir)
CYP3A4 Inducers
Clinical Impact: | The concomitant use of BELBUCA and CYP3A4 inducers can decrease the plasma concentration of buprenorphine [see Clinical Pharmacology (12.3)], potentially resulting in decreased efficacy or onset of a withdrawal syndrome in patients who have developed physical dependence to buprenorphine. After stopping a CYP3A4 inducer, as the effects of the inducer decline, the buprenorphine plasma concentration will increase [see Clinical Pharmacology (12.3)], which could increase or prolong both therapeutic effects and adverse reactions and may cause serious respiratory depression.
Intervention: | If concomitant use is necessary, consider increasing the BELBUCA dosage until stable drug effects are achieved. Evaluate patients for signs of opioid withdrawal. If a CYP3A4 inducer is discontinued, consider BELBUCA dosage reduction and evaluate patients at frequent intervals for signs of respiratory depression and sedation.
Examples: | Rifampin, carbamazepine, phenytoin
Serotonergic Drugs
Clinical Impact: | The concomitant use of opioids with other drugs that affect the serotonergic neurotransmitter system has resulted in serotonin syndrome.
Intervention: | If concomitant use is warranted, frequently evaluate the patient, particularly during treatment initiation and dose adjustment. Discontinue BELBUCA if serotonin syndrome is suspected.
Examples: | Selective serotonin reuptake inhibitors (SSRIs), serotonin and norepinephrine reuptake inhibitors (SNRIs), tricyclic antidepressants (TCAs), triptans, 5-HT3 receptor antagonists, drugs that affect the serotonin neurotransmitter system (e.g., mirtazapine, trazodone, tramadol), certain muscle relaxants (i.e., cyclobenzaprine, metaxalone), monoamine oxidase inhibitors (those intended to treat psychiatric disorders and also others, such as linezolid and intravenous methylene blue).
Monoamine Oxidase Inhibitors (MAOIs)
Clinical Impact: | MAOI interactions with opioids may manifest as serotonin syndrome opioid toxicity (e.g., respiratory depression, coma) [see Warnings and Precautions (5.2)].
Intervention: | The use of BELBUCA is not recommended for patients taking MAOIs or within 14 days of stopping such treatment.
Examples: | phenelzine, tranylcypromine, linezolid
Mixed Agonist/Antagonist and Partial Agonist Opioid Analgesics
Clinical Impact: | May reduce the analgesic effect of BELBUCA and/or precipitate withdrawal symptoms.
Intervention: | Avoid concomitant use.
Examples: | butorphanol, nalbuphine, pentazocine
Muscle Relaxants
Clinical Impact: | Buprenorphine may enhance the neuromuscular blocking action of skeletal muscle relaxants and produce an increased degree of respiratory depression.
Intervention: | Because respiratory depression may be greater than otherwise expected, decrease the dosage of BELBUCA and/or the muscle relaxant as necessary. Due to the risk of respiratory depression with concomitant use of skeletal muscle relaxants and opioids, consider recommending or prescribing an opioid overdose reversal agent [see Dosage and Administration (2.2), Warnings and Precautions (5.2, 5.3)].
Examples: | cyclobenzaprine, metaxalone
Diuretics
Clinical Impact: | Opioids can reduce the efficacy of diuretics by inducing the release of antidiuretic hormone.
Intervention: | Evaluate patients for signs of diminished diuresis and/or effects on blood pressure and increase the dosage of the diuretic as needed.
Anticholinergic Drugs
Clinical Impact: | The concomitant use of anticholinergic drugs may increase the risk of urinary retention and/or severe constipation, which may lead to paralytic ileus.
Intervention: | Evaluate patients for signs of urinary retention or reduced gastric motility when BELBUCA is used concomitantly with anticholinergic drugs.
Antiretrovirals: Nucleoside reverse transcriptase inhibitors (NRTIs)
Clinical Impact: | Nucleoside reverse transcriptase inhibitors (NRTIs) do not appear to induce or inhibit the P450 enzyme pathway, thus no interactions with buprenorphine are expected.
Intervention: | None
Antiretrovirals: Non-nucleoside reverse transcriptase inhibitors (NNRTIs)
Clinical Impact: | Non-nucleoside reverse transcriptase inhibitors (NNRTIs) are metabolized principally by CYP3A4. Efavirenz, nevirapine, and etravirine are known CYP3A inducers, whereas delavirdine is a CYP3A inhibitor. Significant pharmacokinetic interactions between NNRTIs (e.g., efavirenz and delavirdine) and buprenorphine have been shown in clinical studies, but these pharmacokinetic interactions did not result in any significant pharmacodynamic effects.
Intervention: | If prescribing an NNRTI to a patient taking BELBUCA frequently reevaluate for this interaction and adjust dosing as necessary.
Examples: | efavirenz, nevirapine, etravirine, delavirdine
Antiretrovirals: Protease inhibitors (PIs)
Clinical Impact: | Studies have shown some antiretroviral protease inhibitors (PIs) with CYP3A4 inhibitory activity (nelfinavir, lopinavir/ritonavir, ritonavir) have little effect on buprenorphine pharmacokinetics and no significant pharmacodynamic effects. Other PIs with CYP3A4 inhibitory activity (atazanavir and atazanavir/ritonavir) resulted in elevated levels of buprenorphine and norbuprenorphine, and patients in one study reported increased sedation. Symptoms of opioid excess have been found in post-marketing reports of patients receiving buprenorphine and atazanavir with and without ritonavir concomitantly.
Intervention: | Evaluate patients taking BELBUCA and atazanavir with and without ritonavir and reduce the dose of BELBUCA if warranted.
Examples: | atazanavir, ritonavir

8 USE IN SPECIFIC POPULATIONS

8.1 Pregnancy

Risk Summary

Use of opioid analgesics for an extended period of time during pregnancy may cause neonatal opioid withdrawal syndrome [see Warnings and Precautions (5.4)]. There are no adequate and well-controlled studies of BELBUCA or buprenorphine in pregnant women. Limited published data on use of buprenorphine, the active ingredient in BELBUCA, in pregnancy, have not shown an increased risk of major malformations. Reproductive and developmental studies in rats and rabbits identified adverse events at approximately 2 times the maximum recommended human dose (MRHD) of 1.8 mg/day of BELBUCA. Embryofetal death was observed in both rats and rabbits administered buprenorphine during the period of organogenesis at doses approximately 54 and 2.2 times, respectively, the MRHD of 1.8 mg/day of buprenorphine. Pre-and postnatal development studies in rats demonstrated increased neonatal deaths at 2.7 times and above and dystocia at approximately 27 times the MRHD of 1.8 mg/day of buprenorphine. No clear teratogenic effects were seen when buprenorphine was administered during organogenesis with a range of doses 5 times or greater than the MRHD of 1.8 mg/day of buprenorphine. However, increases in skeletal abnormalities were noted in rats and rabbits administered buprenorphine daily during organogenesis at doses approximately 5.4 and 10.8 times the MRHD of 1.8 mg/day of buprenorphine, respectively. In a few studies, some events such as acephalus and omphalocele were also observed but these findings were not clearly treatment-related [see Data].

The background risk of major birth defects and miscarriage for the indicated population is unknown. Adverse outcomes in pregnancy can occur regardless of the health of the mother or the use of medications. In the U.S. general population, the estimated background risk of major birth defects and miscarriage in clinically recognized pregnancies is 2 to 4% and 15 to 20%, respectively.

Clinical Considerations

Fetal/Neonatal Adverse Reactions

Use of opioid analgesics for an extended period of time during pregnancy for medical or nonmedical purposes can result in physical dependence in the neonate and neonatal opioid withdrawal syndrome shortly after birth. Neonatal opioid withdrawal syndrome presents as irritability, hyperactivity and abnormal sleep pattern, high pitched cry, tremor, vomiting, diarrhea, and failure to gain weight. The onset, duration, and severity of neonatal opioid withdrawal syndrome vary based on the specific opioid used, duration of use, timing and amount of last maternal use, and rate of elimination of the drug by the newborn. Observe newborns for symptoms of neonatal opioid withdrawal syndrome and manage accordingly [see Warnings and Precautions (5.4)].

Labor or Delivery

Opioids cross the placenta and may produce respiratory depression and psycho-physiologic effects in neonates. An opioid overdose reversal agent, such as naloxone or nalmefene, must be available for reversal of opioid-induced respiratory depression in the neonate. BELBUCA is not recommended for use in women immediately prior to labor, when shorter-acting analgesics or other analgesic techniques are more appropriate. Opioid analgesics, including BELBUCA, can prolong labor through actions which temporarily reduce the strength, duration, and frequency of uterine contractions. However, this effect is not consistent and may be offset by an increased rate of cervical dilation, which tends to shorten labor.

Data

Animal Data

The exposure margins listed below are based on body surface area comparisons (mg/m^2) to MRHD of 1.8 mg buprenorphine via BELBUCA.

Following oral administration to rats no teratogenic effects were observed at buprenorphine doses up to 250 mg/kg/day (estimated exposure approximately 1351 times the MRHD of 1.8 mg). Following oral administration to rabbits, no teratogenic effects were observed at buprenorphine doses up to 40 mg/kg/day (estimated exposure approximately 432 times the MRHD of 1.8 mg). No definitive drug-related teratogenic effects were observed in rats and rabbits at IM doses up to 30 mg/kg/day (estimated exposure approximately 161 times and 324 times, respectively, the MRHD of 1.8 mg). Acephalus was observed in one rabbit fetus from the low-dose group and omphalocele was observed in two rabbit fetuses from the same litter in the mid-dose group; no findings were observed in fetuses from the high-dose group. Following oral administration of buprenorphine to rats, dose-related post-implantation losses, evidenced by increases in the numbers of early resorptions with consequent reductions in the numbers of fetuses, were observed at doses of 10 mg/kg/day or greater (estimated exposure approximately 54 times the MRHD of 1.8 mg).

In the rabbit, increased post-implantation losses occurred at an oral dose of 40 mg/kg/day. Following IM administration in the rat and the rabbit, post-implantation losses, as evidenced by decreases in live fetuses and increases in resorptions, occurred at 30 mg/kg/day.

Buprenorphine was not teratogenic in rats or rabbits after IM or subcutaneous (SC) doses up to 5 mg/kg/day (estimated exposure was approximately 27 and 54 times, respectively, the MRHD of 1.8 mg), after IV doses up to 0.8 mg/kg/day (estimated exposure was approximately 4.3 and 8.7 times, respectively, the MRHD of 1.8 mg), or after oral doses up to 160 mg/kg/day in rats (estimated exposure was approximately 865 times the MRHD of 1.8 mg) and 25 mg/kg/day in rabbits (estimated exposure was approximately 270 times the MRHD of 1.8 mg). Significant increases in skeletal abnormalities (e.g., extra thoracic vertebra or thoraco-lumbar ribs) were noted in rats after SC administration of 1 mg/kg/day and up (estimated exposure was approximately 5.4 times the MRHD of 1.8 mg), but were not observed at oral doses up to 160 mg/kg/day.

Increases in skeletal abnormalities in rabbits after IM administration of 5 mg/kg/day (estimated exposure was approximately 54 times the MRHD of 1.8 mg) or oral administration of 1 mg/kg/day or greater (estimated exposure was approximately 10.8 times the MRHD of 1.8 mg) were not statistically significant.

In rabbits, buprenorphine produced statistically significant pre-implantation losses at oral doses of 1 mg/kg/day or greater and post-implantation losses that were statistically significant at IV doses of 0.2 mg/kg/day or greater (estimated exposure approximately 2.2 times the MRHD of 1.8 mg).

Dystocia was noted in pregnant rats treated intramuscularly with buprenorphine during gestation and lactation at 5 mg/kg/day (approximately 27 times the MRHD of 1.8 mg). Fertility, pre-, and post-natal development studies with buprenorphine in rats indicated increases in neonatal mortality after oral doses of 0.8 mg/kg/day and up (approximately 4.3 times the MRHD of 1.8 mg), after IM doses of 0.5 mg/kg/day and up (approximately 2.7 times the MRHD of 1.8 mg), and after SC doses of 0.1 mg/kg/day and up (approximately 0.5 times the MRHD of 1.8 mg). An apparent lack of milk production during these studies likely contributed to the decreased pup viability and lactation indices. Delays in the occurrence of righting reflex and startle response were noted in rat pups at an oral dose of 80 mg/kg/day (approximately 432 times the MRHD of 1.8 mg).

8.2 Lactation

Risk Summary

Based on two studies in 13 lactating women being treated for opioid dependence and their breastfed infants, buprenorphine and its metabolite norbuprenorphine are present in low levels in human milk and infant urine, and available data have not shown adverse reactions in breastfed infants [see Data]. There are no data on the effects of BELBUCA on milk production. Because of the potential for serious adverse reactions, including excess sedation and respiratory depression in a breastfed infant, advise patients that breastfeeding is not recommended during treatment with BELBUCA.

Clinical Considerations

Monitor infants exposed to BELBUCA through breast milk for excess sedation and respiratory depression. Withdrawal symptoms can occur in breastfed infants when maternal administration of buprenorphine is stopped or when breastfeeding is stopped.

Data

Based on limited data from a study of six lactating women being treated for opioid dependence who were taking a median oral dose of buprenorphine of 0.29 mg/kg/day 5-8 days after delivery, breast milk contained a median infant dose of 0.42 mcg/kg/day of buprenorphine and 0.33 mcg/kg/day of norbuprenorphine, which are equal to 0.2% and 0.12% of the maternal weight-adjusted dose. The median concentrations of buprenorphine and norbuprenorphine in infant urine were 1.0 nmol/L and 2.3 nmol/L, respectively.

Based on limited data from a study of seven lactating women being treated for opioid dependence who were taking a median oral dose of buprenorphine of 7 mg/day an average of 1.12 months after delivery, the mean milk concentrations of buprenorphine and norbuprenorphine were 3.65 mcg/L and 1.94 mcg/L, respectively. Based on the limited data from this study, and assuming milk consumption of 150 mL/kg/day, an exclusively breastfed infant would receive an estimated mean of 0.55 mcg/kg/day of buprenorphine and 0.29 mcg/kg/day of norbuprenorphine, which are 0.38% and 0.18% of the maternal weight-adjusted dose.

No adverse reactions were observed in the infants in these two studies.

8.3 Females and Males of Reproductive Potential

Infertility

Use of opioids for an extended period of time may cause reduced fertility in females and males of reproductive potential. It is not known whether these effects on fertility are reversible [see Adverse Reactions (6.2), Clinical Pharmacology (12.2), Nonclinical Toxicology (13.1)].

8.4 Pediatric Use

The safety and efficacy of BELBUCA have not been established in pediatric patients.

8.5 Geriatric Use

Of the total number of patients that were treated with BELBUCA in controlled and open-label chronic pain trials (2,127), 340 patients were 65 years and older. Of those, 49 patients were aged 75 years and older. The incidences of selected BELBUCA-related adverse effects were higher in older subjects.

No notable differences in pharmacokinetics were observed from population pharmacokinetic analysis in subjects aged 65 and older compared to younger subjects. Other reported clinical experience with buprenorphine has not identified differences in responses between the elderly and younger patients. Although specific dose adjustments on the basis of advanced age are not required for pharmacokinetic reasons, use caution in the elderly population to ensure safe use.

Respiratory depression is the chief risk for elderly patients treated with opioids and has occurred after large initial doses were administered to patients who were not opioid-tolerant or when opioids were co-administered with other agents that depress respiration. Titrate the dosage of BELBUCA slowly in geriatric patients and frequently reevaluate the patient for signs of central nervous system and respiratory depression [see Warnings and Precautions (5.7), Clinical Pharmacology (12.3)].

Buprenorphine is known to be substantially excreted by the kidney, and the risk of adverse reactions to this drug may be greater in patients with impaired renal function. Because elderly patients are more likely to have decreased renal function, care should be taken in dose selection, and it may be useful to regularly evaluate renal function.

8.6 Hepatic Impairment

BELBUCA has not been evaluated in patients with severe hepatic impairment.

The effects of hepatic impairment on the pharmacokinetics of buprenorphine were evaluated in a pharmacokinetic study. Buprenorphine is extensively metabolized in the liver and buprenorphine plasma levels were found to be higher and the half-life was found to be longer in subjects with moderate and severe hepatic impairment, but not in subjects with mild hepatic impairment.

Given that increased buprenorphine plasma levels are associated with a greater risk of toxicity and overdose, a dosage reduction in patients with severe hepatic impairment (i.e., Child-Pugh C) is recommended [see Dosage and Administration (2.6)]. Regularly evaluate patients with severe hepatic impairment for signs and symptoms of overdose. A dosage reduction in patients with moderate hepatic impairment (Child-Pugh B) is not needed; however, regularly evaluate these patients for signs and symptoms of toxicity or overdose. A dosage reduction in patients with mild hepatic impairment (Child-Pugh A) is not needed [see Dosage and Administration (2.6), Warnings and Precautions (5.19), Clinical Pharmacology (12.3)].

9 DRUG ABUSE AND DEPENDENCE

9.1 Controlled Substance

BELBUCA contains buprenorphine hydrochloride, a Schedule III controlled substance.

9.2 Abuse

BELBUCA contains buprenorphine, a substance with high potential for misuse and abuse, which can lead to the development of substance use disorder, including addiction [see Warnings and Precautions (5.1)].

Misuse is the intentional use, for therapeutic purposes, of a drug by an individual in a way other than prescribed by a healthcare provider or for whom it was not prescribed.

Abuse is the intentional, non-therapeutic use of a drug, even once, for its desirable psychological or physiological effects.

Drug addiction is a cluster of behavioral, cognitive, and physiological phenomena that may include a strong desire to take the drug, difficulties in controlling drug use (e.g., continuing drug use despite harmful consequences, giving a higher priority to drug use than other activities and obligations), and possible tolerance or physical dependence.

Misuse and abuse of BELBUCA increases risk of overdose, which may lead to central nervous system and respiratory depression, hypotension, seizures, and death. The risk is increased with concurrent abuse of BELBUCA with alcohol and/or other CNS depressants. Abuse of and addiction to opioids in some individuals may not be accompanied by concurrent tolerance and symptoms of physical dependence. In addition, abuse of opioids can occur in the absence of addiction.

All patients treated with opioids require careful and frequent reevaluation for signs of misuse, abuse, and addiction, because use of opioid analgesic products carries the risk of addiction even under appropriate medical use. Patients at high risk of BELBUCA abuse include those with a history of prolonged use of any opioid, including products containing buprenorphine, those with a history of drug or alcohol abuse, or those who use BELBUCA in combination with other abused drugs.

"Drug-seeking" behavior is very common in persons with substance use disorders. Drug-seeking tactics include emergency calls or visits near the end of office hours, refusal to undergo appropriate examination, testing, or referral, repeated "loss" of prescriptions, tampering with prescriptions, and reluctance to provide prior medical records or contact information for other treating healthcare provider(s). "Doctor shopping" (visiting multiple prescribers to obtain additional prescriptions) is common among people who abuse drugs and people with substance use disorder. Preoccupation with achieving adequate pain relief can be appropriate behavior in a patient with inadequate pain control.

BELBUCA, like other opioids, can be diverted for nonmedical use into illicit channels of distribution. Careful record-keeping of prescribing information, including quantity, frequency, and renewal requests, as required by state and federal law, is strongly advised.

Proper assessment of the patient, proper prescribing practices, periodic reevaluation of therapy, and proper dispensing and storage are appropriate measures that help to limit abuse of opioid drugs.

Risks Specific to Abuse of BELBUCA

Abuse of BELBUCA poses a risk of overdose and death. This risk is increased with concurrent use of BELBUCA with alcohol and/or other substances, including other opioids and benzodiazepines [see Warnings and Precautions (5.1, 5.3), Drug Interactions (7)].

BELBUCA is approved for buccal use only. Intentional compromise of the buccal film might result in the uncontrolled delivery of buprenorphine and pose a significant risk to the abuser that could result in overdose and death [see Warnings and Precautions (5.1)]. Abuse may occur by applying the buccal film in the absence of legitimate purpose, or by chewing, swallowing, snorting, or injecting buprenorphine extracted from the buccal film.

Parenteral drug abuse is commonly associated with transmission of infectious diseases such as hepatitis and HIV.

9.3 Dependence

Both tolerance and physical dependence can develop during use of opioid therapy.

Tolerance is a physiological state characterized by a reduced response to a drug after repeated administration (i.e., a higher dose of a drug is required to produce the same effect that was once obtained at a lower dose).

Physical dependence is a state that develops as a result of a physiological adaptation in response to repeated drug use, manifested by withdrawal signs and symptoms after abrupt discontinuation or a significant dose reduction of a drug.

Withdrawal may be precipitated through the administration of drugs with opioid antagonist activity (e.g., naloxone, nalmefene), mixed agonist/antagonist analgesics (e.g., pentazocine, butorphanol, nalbuphine), or partial agonists (e.g., buprenorphine). Physical dependence may not occur to a clinically significant degree until after several days to weeks of continued use.

Do not rapidly reduce or abruptly discontinue BELBUCA in a patient physically dependent on opioids. Rapid tapering of BELBUCA in a patient physically dependent on opioids may lead to serious withdrawal symptoms, uncontrolled pain, and suicide. Rapid discontinuation has also been associated with attempts to find other sources of opioid analgesics, which may be confused with drug-seeking for abuse.

When discontinuing BELBUCA, gradually taper the dosage using a patient-specific plan that considers the following: the dose of BELBUCA the patient has been taking, the duration of treatment, and the physical and psychological attributes of the patient. To improve the likelihood of a successful taper and minimize withdrawal symptoms, it is important that the opioid tapering schedule is agreed upon by the patient. In patients taking opioids for an extended period of time at high doses, ensure that a multimodal approach to pain management, including mental health support (if needed), is in place prior to initiating an opioid analgesic taper [see Dosage and Administration (2.5), Warnings and Precautions (5.17)].

Infants born to mothers physically dependent on opioids will also be physically dependent and may exhibit respiratory difficulties and withdrawal signs [see Use in Specific Populations (8.1)].

10 OVERDOSAGE

Clinical Presentation

Acute overdosage with buprenorphine is manifested by respiratory depression, somnolence progressing to stupor or coma, skeletal muscle flaccidity, cold and clammy skin, constricted pupils, and, in some cases, pulmonary edema, bradycardia, hypotension, hypoglycemia, partial or complete airway obstruction, atypical snoring, and death. Marked mydriasis rather than miosis may be seen due to severe hypoxia in overdose situations [see Clinical Pharmacology (12.2)]. Toxic leukoencephalopathy has been reported after opioid overdose and can present hours, days, or weeks after apparent recovery from the initial intoxication.

Treatment of Overdose

In case of overdose, priorities are the re-establishment of a patent and protected airway and institution of assisted or controlled ventilation, if needed. Employ other supportive measures (including oxygen, vasopressors) in the management of circulatory shock and pulmonary edema, as indicated. Cardiac arrest or arrhythmias will require advanced life support measures.

Naloxone may not be effective in reversing any respiratory depression produced by buprenorphine. High doses of naloxone, 10-35 mg/70 kg, may be of limited value in the management of buprenorphine overdose. The onset of naloxone effect may be delayed by 30 minutes or more.

Because the duration of reversal would be expected to be less than the duration of action of buprenorphine from BELBUCA, carefully monitor the patient until spontaneous respiration is reliably re-established. Even in the face of improvement, continued medical monitoring is required for at least 24 hours because of the possibility of extended effects of buprenorphine.

In an individual physically dependent on opioids, administration of an opioid overdose reversal agent may precipitate an acute withdrawal. The severity of the withdrawal symptoms experienced will depend on the degree of physical dependence and the dose of the reversal agent administered. If a decision is made to treat serious respiratory depression in the physically dependent patient, administration of the reversal agent should be initiated with care and by titration with smaller than usual doses of the reversal agent.

11 DESCRIPTION

BELBUCA is a buccal film that provides transmucosal delivery of buprenorphine, a partial opioid agonist. BELBUCA is a rectangular bi-layer, peppermint-flavored, buccal film with rounded corners, consisting of a white to off-white backing layer with strength identifier printed in black ink and a light yellow to yellow active mucoadhesive layer containing buprenorphine hydrochloride. The yellow side of the film is applied to the inside of the cheek where it adheres to the moist buccal mucosa to deliver the drug as the film dissolves.

Buprenorphine hydrochloride USP is the active ingredient in BELBUCA. The chemical name of buprenorphine hydrochloride is 6,14-ethenomorphinan-7-methanol, 17-(cyclopropylmethyl)- α-(1,1-dimethylethyl)-4, 5-epoxy-18,19-dihydro-3-hydroxy-6-methoxy-α-methyl-, hydrochloride, [5α, 7α, (S)]. Its structural formula is as follows:

The molecular weight of buprenorphine hydrochloride is 504.10; the empirical formula is C29H41NO4∙HCl. Buprenorphine hydrochloride occurs as a white or off-white crystalline powder. It is sparingly soluble in water, freely soluble in methanol, soluble in alcohol, and practically insoluble in cyclohexane. The pKa is 8.5 for the amine function and 10.0 for the phenol function.

Dosage strengths of BELBUCA are based on the active moiety, buprenorphine. BELBUCA is available as 75 mcg, 150 mcg, 300 mcg, 450 mcg, 600 mcg, 750 mcg, and 900 mcg buprenorphine per film. The strength of each film is dependent on the buprenorphine concentration in the formulation and the surface area of the film.

Table 6 lists the dosage strength, equivalent amount of buprenorphine hydrochloride USP (active ingredient), unique identifier and film size for each strength.

Table 6: BELBUCA Identifier and Film Size
Buprenorphine Strength (mcg) | Buprenorphine Hydrochloride (mcg) | BELBUCA Identifier | Film Size (cm^2)
75 | 80.9 | E0 | 1.215
150 | 161.8 | E1 | 2.431
300 | 323.4 | E3 | 0.934
450 | 485.1 | E4 | 1.400
600 | 646.8 | E6 | 1.867
750 | 808.5 | E7 | 2.334
900 | 970.2 | E9 | 2.801

Each buccal film also contains carboxymethylcellulose sodium USP, citric acid anhydrous USP, hydroxyethylcellulose NF, hydroxypropylcellulose NF, methylparaben NF, monobasic sodium phosphate anhydrous USP, peppermint oil NF, polycarbophil USP, propylene glycol USP, propylparaben NF, sodium benzoate NF, sodium hydroxide NF, saccharin sodium NF, titanium dioxide USP, vitamin E acetate USP, yellow iron oxide, purified water USP, and TekPrint SW-9008 black ink (shellac NF, black iron oxide NF).

12 CLINICAL PHARMACOLOGY

12.1 Mechanism of Action

Buprenorphine is a partial agonist at the mu-opioid receptor and an antagonist at the kappa-opioid receptor.

12.2 Pharmacodynamics

Effects on the Central Nervous System

The principal action of therapeutic value of buprenorphine is analgesia and is thought to be due to buprenorphine binding with high affinity to opioid receptors on neurons in the brain and spinal cord.

Buprenorphine produces respiratory depression by direct action on brain stem respiratory centers. The respiratory depression involves a reduction in the responsiveness of the brain stem respiratory centers to both increases in carbon dioxide tension and electrical stimulation.

Buprenorphine causes miosis, even in total darkness. Pinpoint pupils are a sign of opioid overdose but are not pathognomonic (e.g., pontine lesions of hemorrhagic or ischemic origins may produce similar findings). Marked mydriasis rather than miosis may be seen with worsening hypoxia in the setting of buprenorphine overdose.

Unlike other opioids, buprenorphine appears to exhibit a dose-ceiling effect.

Effects on the Gastrointestinal Tract and Other Smooth Muscle

Buprenorphine causes a reduction in motility associated with an increase in tone in the stomach and duodenum. Digestion of food in the small intestine is delayed and propulsive contractions are decreased. Propulsive peristaltic waves in the colon are decreased, while tone is increased to the point of spasm, resulting in constipation. Buprenorphine may cause an increase in biliary tract pressure as a result of spasm of the sphincter of Oddi. Other opioid-induced effects may include a reduction in biliary and pancreatic secretions, spasm of sphincter of Oddi, transient elevations in serum amylase, and opioid-induced esophageal dysfunction (OIED).

Effects on the Cardiovascular System

Buprenorphine produces peripheral vasodilation, which may result in orthostatic hypotension or syncope. Manifestations of histamine release and/or peripheral vasodilation may include pruritus, flushing, red eyes, sweating, and/or orthostatic hypotension.

Effects on Cardiac Electrophysiology

QTc prolongation with BELBUCA has been observed. Of the 1590 patients that were treated with BELBUCA in controlled and open-label chronic pain trials at doses up to 900 mcg every 12 hours, 2% demonstrated a prolongation of QTcF to a post-baseline value between 450 - 480 msec during therapy.

Effects on the Endocrine System

Opioids inhibit the secretion of adrenocorticotropic hormone (ACTH), cortisol, and luteinizing hormone (LH) in humans [see Adverse Reactions (6.2)]. They also stimulate prolactin, growth hormone (GH) secretion, and pancreatic secretion of insulin and glucagon.

Use of opioids for an extended period of time may influence the hypothalamic-pituitary-gonadal axis, leading to androgen deficiency that may manifest as low libido, impotence, erectile dysfunction, amenorrhea, or infertility. The causal role of opioids in the clinical syndrome of hypogonadism is unknown because the various medical, physical, lifestyle, and psychological stressors that may influence gonadal hormone levels have not been adequately controlled for in studies conducted to date [see Adverse Reactions (6.2)].

Effects on the Immune System

Opioids have been shown to have a variety of effects on components of the immune system in in vitro and animal models. The clinical significance of these findings is unknown. Overall, the effects of opioids appear to be modestly immunosuppressive.

Concentration–Efficacy Relationships

The minimum effective analgesic concentration varies widely among patients, especially among patients who have been previously treated with opioid agonists. The minimum effective analgesic concentration of buprenorphine for any individual patient may increase over time due to an increase in pain, the development of a new pain syndrome, and/or the development of analgesic tolerance [see Dosage and Administration (2.1, 2.4)].

Concentration–Adverse Reaction Relationships

There is a relationship between increasing buprenorphine plasma concentration and increasing frequency of dose-related opioid adverse reactions such as nausea, vomiting, CNS effects, and respiratory depression. In opioid-tolerant patients, the situation may be altered by the development of tolerance to opioid-related adverse reactions [see Dosage and Administration (2.1, 2.3, 2.4)].

12.3 Pharmacokinetics

Absorption

Systemic plasma levels of buprenorphine increased in a linear manner (Cmax and AUC) over the single dose range of 75 to 1200 mcg as shown in Table 7. The absolute bioavailability of BELBUCA ranged from 46 to 65%.

Table 7: Mean (± SD) BELBUCA Pharmacokinetic Parameters
Regimen | Dosage (mcg) | Cmax (ng/mL) | AUC0-t (h∙ng/mL) | AUC0-∞ (h∙ng/mL) | Tmax [Tmax values reported as median and range] (hr)
Single Dose | 75 | 0.17±0.30 | 0.46±0.22 | 0.63±0.24 | 3.00 (1.50-4.00)
Single Dose | 300 | 0.47±0.47 | 2.00±0.68 | 2.3±0.68 | 2.50 (0.50-4.00)
Single Dose | 1200 | 1.43±0.45 | 9.6±2.9 | 10.5±3.32 | 3.00 (1.00-4.00)

Following the multiple dose administration (60 to 240 mcg every 12 hours) of BELBUCA, apparent steady-state buprenorphine plasma concentrations were achieved prior to the 6th dose. Buprenorphine steady-state Cmax and AUC increased proportional to dose.

Systemic exposure to buprenorphine from BELBUCA film was reduced by 23-27% by the ingestion of liquids (cold, hot and room temperature water) during film administration; additionally, coadministration with low pH liquid, such as decaffeinated cola, decreased buprenorphine exposure from BELBUCA by approximately 37%. The consumption of liquids should be avoided until the buccal film has completely dissolved [see Dosage and Administration (2.8)].

Distribution

Buprenorphine is approximately 96% protein bound, primarily to alpha and beta globulin.

Elimination

Metabolism

Buprenorphine undergoes both N-dealkylation to norbuprenorphine and glucuronidation. The N-dealkylation pathway is mediated primarily by CYP3A4. Norbuprenorphine, the major metabolite, can further undergo glucuronidation. Norbuprenorphine has been found to bind to opioid receptors in vitro; however, it has not been studied clinically for opioid-like activity.

Excretion

A mass balance study of buprenorphine showed complete recovery of radiolabel in urine (30%) and feces (69%) collected up to 11 days after dosing. Almost all of the dose was accounted for in terms of buprenorphine, norbuprenorphine, and two unidentified buprenorphine metabolites. In urine, most of buprenorphine and norbuprenorphine was conjugated (buprenorphine, 1% free and 9.4% conjugated; norbuprenorphine, 2.7% free and 11% conjugated). In feces, almost all of the buprenorphine and norbuprenorphine was free (buprenorphine, 33% free and 5% conjugated; norbuprenorphine, 21% free and 2% conjugated).

Based on multiple-dose studies performed with BELBUCA, the mean plasma elimination half-life of buprenorphine was 27.6±11.2 hours.

Drug Interaction Studies

CYP3A4 Inhibitors and Inducers

Buprenorphine undergoes N-dealkylation mediated primarily by CYP3A4, so its metabolism can be inhibited by CYP3A4 inhibitors. The interaction of buprenorphine with all CYP3A4 inducers has not been studied [see Drug Interactions (7)].

Buprenorphine has been found to be a CYP2D6 and CYP3A4 inhibitor and its major metabolite, norbuprenorphine, has been found to be a moderate CYP2D6 inhibitor in in vitro studies employing human liver microsomes. However, the relatively low plasma concentrations of buprenorphine and norbuprenorphine resulting from therapeutic doses are not expected to raise significant drug-drug interaction concerns.

Specific Populations

Age: Geriatric Patients

No notable differences in pharmacokinetics were observed from population PK analysis in subjects aged 65 and older compared to younger subjects. Other reported clinical experience with buprenorphine has not identified differences in responses between the elderly and younger patients.

Sex

No notable sex differences in pharmacokinetics were observed from population PK analysis.

Renal Impairment

No studies in patients with renal impairment have been performed with BELBUCA. In an independent study, the effect of impaired renal function on buprenorphine pharmacokinetics after IV bolus and after continuous IV infusion administration was evaluated and no notable differences in plasma buprenorphine concentrations were identified in patients with normal renal function compared to impaired renal function or renal failure.

Hepatic Impairment

BELBUCA has not been evaluated in patients with severe hepatic impairment. The pharmacokinetics of buprenorphine following an IV infusion of 0.3 mg of buprenorphine were compared in 8 patients with mild hepatic impairment (Child-Pugh A), 4 patients with moderate impairment (Child-Pugh B), and 12 subjects with normal hepatic function. Buprenorphine and norbuprenorphine plasma levels did not increase in mild or moderately impaired patient cohorts.

In another pharmacokinetic study, the disposition of buprenorphine was determined after administering a 2.0/0.5 mg buprenorphine/naloxone sublingual tablet in subjects with varied degrees of hepatic impairment as indicated by Child-Pugh criteria. The disposition of buprenorphine in patients with hepatic impairment was compared to disposition in subjects with normal hepatic function. In subjects with mild hepatic impairment, the changes in mean Cmax, AUC0-last, and half-life values of buprenorphine were not clinically significant. No dose adjustment is needed in patients with mild hepatic impairment.

For subjects with moderate and severe hepatic impairment, mean Cmax, AUC0-last, and half-life values of buprenorphine were increased (Table 8) [see Dosage and Administration (2.6), Warnings and Precautions (5.19), Use in Specific Populations (8.6)].

Table 8: Changes in Pharmacokinetic Parameters in Subjects with Moderate and Severe Hepatic Impairment
Hepatic Impairment | PK Parameters | Increase in buprenorphine compared to healthy subjects
Moderate | Cmax | 8%
Moderate | AUC0-last | 64%
Moderate | Half-life | 35%
Severe | Cmax | 72%
Severe | AUC0-last | 181%
Severe | Half-life | 57%

Oral Mucositis

In an open-label pharmacokinetic study in 6 cancer patients with Grade 3 mucositis, buprenorphine was absorbed more rapidly from BELBUCA resulting in a higher Cmax (~79%) and AUC (~56%) compared to age- and gender-matched healthy control subjects [see Dosage and Administration (2.7), Warnings and Precautions (5.20)].

13 NONCLINICAL TOXICOLOGY

13.1 Carcinogenesis, Mutagenesis, Impairment of Fertility

Carcinogenesis

Carcinogenicity studies of buprenorphine were conducted in Sprague-Dawley rats and CD-1 mice. Buprenorphine was administered in the diet to rats at doses of 0.6, 5.5, and 56 mg/kg/day for 27 months (estimated exposure was approximately 3, 29, and 299 times the maximum recommended human dose (MRHD) of buccal BELBUCA of 1.8 mg on a mg/m^2 basis, respectively). Statistically significant dose-related increases in testicular interstitial (Leydig's) cell tumors occurred. In an 86-week study in CD-1 mice, buprenorphine was not carcinogenic at dietary doses up to 100 mg/kg/day (estimated exposure was approximately 267 times the MRHD).

Mutagenesis

Buprenorphine was studied in a series of tests utilizing gene, chromosome, and DNA interactions in both prokaryotic and eukaryotic systems. Results were negative in yeast (S. cerevisiae) for recombinant, gene convertant, or forward mutations; negative in Bacillus subtilis "rec" assay, negative for clastogenicity in CHO cells, Chinese hamster bone marrow and spermatogonia cells, and negative in the mouse lymphoma L5178Y assay.

Results were equivocal in the Ames test: negative in studies in two laboratories, but positive for frame shift mutation at a high dose (5 mg/plate) in a third study. Results were positive in the Green-Tweets (E. coli) survival test, positive in a DNA synthesis inhibition (DSI) test with testicular tissue from mice, for both in vivo and in vitro incorporation of [^3H]thymidine, and positive in an unscheduled DNA synthesis (UDS) test using testicular cells from mice.

Impairment of Fertility

Reproduction studies of buprenorphine in rats demonstrated no evidence of impaired fertility at daily oral doses up to 80 mg/kg/day (estimated exposure approximately 427 times the MRHD) or up to 5 mg/kg/day IM or SC (estimated exposure was approximately 27 times the MRHD).

14 CLINICAL STUDIES

The efficacy of BELBUCA has been evaluated in three 12-week double-blind, placebo-controlled clinical trials in patients who were not opioid tolerant and opioid-experienced patients with moderate-to-severe chronic low back pain using pain scores as the primary efficacy variable. Two of these studies, described below, demonstrated efficacy in patients with low back pain. One study in low back pain did not show a statistically significant pain reduction for BELBUCA compared to placebo.

12-Week Study in Patients who were not Opioid Tolerant with Chronic Low Back Pain

A total of 749 patients with chronic low back pain entered an open-label, dose-titration period for up to eight weeks. Potential subjects were excluded from participation for QTcF interval of 450 ms or more, hypokalemia, clinically unstable cardiac disease, a history of Long QT Syndrome or an immediate family member with this condition, or taking Class IA or Class III antiarrhythmic medications. Patients initiated therapy with a single 75 mcg dose of BELBUCA on Day 1 and continued taking BELBUCA 75 mcg either once daily or every 12 hours for 4-8 days as tolerated. The dose was then increased to 150 mcg every 12 hours, and patients could continue to dose escalate in 150 mcg dose increments every 4-8 days for up to 6 weeks if the adverse effects were tolerable and the analgesic effects were not adequate. Patients who achieved adequate analgesia and tolerable adverse effects on BELBUCA for at least 2 weeks were then randomized to continue their titrated dose of BELBUCA or matching placebo buccal film. Sixty-one percent (61%) of the patients who entered the open-label dose titration period were able to titrate to a tolerable and effective dose and were randomized into a 12-week, double-blind treatment period. Fifteen percent of patients discontinued due to an adverse event and 4% discontinued due to lack of a therapeutic effect. The remaining 20% of patients discontinued due to various non-drug related administrative reasons.

During the first 2 weeks of double-blind treatment, patients were allowed up to 2 tablets per day of hydrocodone/acetaminophen 5/325 mg as supplemental analgesia to minimize opioid withdrawal symptoms in patients randomized to placebo. Thereafter, the supplemental analgesia was limited to 1 to 2 tablets of acetaminophen 500 mg per day. Seventy-six percent of the patients treated with BELBUCA completed the 12-week treatment compared to 73% of the patients treated with placebo. Of the 209 patients randomized to BELBUCA, 4% discontinued due to lack of efficacy and 8% due to adverse events. Of the 211 patients randomized to placebo, 11% discontinued due to lack of efficacy and 4% due to adverse events.

Of the patients who were randomized, the mean pain (SD) scores on a 0 to 10 numeric rating scale (NRS) were 7.1 (1.06) and 7.2 (1.05) prior to open-label titration and 2.8 (1.01) and 2.8 (1.12) at the beginning of the double-blind period for BELBUCA and placebo, respectively. The change from double-blind baseline to week 12 in mean pain (SD) NRS score was statistically significant favoring patients treated with BELBUCA compared with patients treated with placebo.

A higher proportion of BELBUCA patients (62%) had at least a 30% reduction in pain score from prior to open-label titration to study endpoint when compared to patients who received placebo buccal film (47%). A higher proportion of BELBUCA patients (41%) also had at least a 50% reduction in pain score from prior to open-label titration to study endpoint compared to patients who received placebo (33%).

The proportion of patients with various degrees of improvement, from prior to open-label titration (Titration-Baseline) to study endpoint, is shown in Figure 1.

Figure 1: Percentage Improvement in Pain Intensity from Titration-Baseline to Week 12

12-Week Study in Opioid-Experienced Patients with Chronic Low Back Pain

Eight hundred and ten (810) patients on chronic opioid therapy (total daily dose 30-160 mg in oral morphine sulfate equivalents (MSE) for at least 4 weeks) entered an open-label, dose-titration period with BELBUCA for up to 8 weeks, following taper of their prior opioids to 30 mg oral MSE daily. Potential subjects were excluded from participation for QTcF interval of 450 ms or more, hypokalemia, clinically unstable cardiac disease, a history of Long QT Syndrome or an immediate family member with this condition, or taking Class IA or Class III antiarrhythmic medications. Patients were initiated with BELBUCA 150 mcg every 12 hours if they were on 30 to 89 mg oral MSE daily and 300 mcg every 12 hours if they were on 90 to 160 mg oral MSE daily prior to taper. If a patient tolerated the adverse events and the analgesic effects were not adequate, the dose was increased in increments of 150 mcg every 12 hours after 4 to 8 days for up to 6 weeks. Patients were permitted to take hydrocodone/acetaminophen 5/325 mg as analgesic rescue as needed up to a maximum of 4 doses per day during the open-label dose titration period. After a dose was reached with adequate analgesia and tolerable adverse effects for a period of 2 weeks, patients were randomized to continue their titrated dose of BELBUCA or matching placebo. Sixty-three percent (63%) of the patients who entered the open-label titration period were able to titrate to a tolerable and effective dose and were randomized into a 12-week double-blind treatment phase. Ten percent (10%) of patients discontinued due to an adverse event, 8% discontinued due to lack of a therapeutic effect, and 0.1% discontinued due to opioid withdrawal during the open-label titration period. The remaining 20% of patients discontinued due to various non-drug related administrative reasons.

During the double-blind period, patients were permitted to take up to 2 doses of 5/325 mg or 10/650 mg of hydrocodone/acetaminophen per day for the first 2 weeks to minimize opioid withdrawal symptoms in patients randomized to placebo. After the first 2 weeks, patients were permitted to take 1 dose of 5/325 mg or 10/650 mg per day. Eighty-three percent of patients treated with BELBUCA and 57% of patients treated with placebo buccal film completed the 12-week treatment period. Of the 243 patients randomized to BELBUCA, 8% discontinued due to lack of efficacy and 2% due to adverse events. Of the 248 patients randomized to placebo buccal film, 25% discontinued due to lack of efficacy and 5% due to adverse events.

Of the patients who were randomized into the double-blind period, the mean pain (SD) NRS scores were 6.8 (1.28) and 6.6 (1.32) prior to open-label titration and 2.9 (0.985) and 2.8 (1.05) at the beginning of the double-blind period for BELBUCA and placebo, respectively. The change from baseline to week 12 in mean pain (SD) NRS score was statistically significant in favor of patients treated with BELBUCA compared with patients treated with placebo.

A higher proportion of BELBUCA patients (64%) had at least a 30% reduction in pain score from prior to open-label titration to study endpoint when compared to patients who received placebo buccal film (31%). A higher proportion of BELBUCA patients (39%) also had at least a 50% reduction in pain score from prior to open-label titration to study endpoint compared to patients who received placebo (17%).

The proportion of patients with various degrees of improvement from prior to open-label titration (Titration-Baseline) to study endpoint is shown in Figure 2.

Figure 2: Percentage Improvement in Pain Intensity from Titration-Baseline to Week 12

16 HOW SUPPLIED/STORAGE AND HANDLING

BELBUCA (buprenorphine buccal film) films are supplied in cartons containing 60 individual child-resistant foil packages as follows:

Strength | NDC Number Carton | NDC Number Foil Package | Foil Color
The 75 mcg buccal film is printed with E0 | 59385-021-60 | 59385-021-01 | Red
The 150 mcg buccal film is printed with E1 | 59385-022-60 | 59385-022-01 | Green
The 300 mcg buccal film is printed with E3 | 59385-023-60 | 59385-023-01 | Gray
The 450 mcg buccal film is printed with E4 | 59385-024-60 | 59385-024-01 | Purple
The 600 mcg buccal film is printed with E6 | 59385-025-60 | 59385-025-01 | Blue
The 750 mcg buccal film is printed with E7 | 59385-026-60 | 59385-026-01 | Light Blue
The 900 mcg buccal film is printed with E9 | 59385-027-60 | 59385-027-01 | Orange

STORAGE AND HANDLING

Store at 20°C to 25°C (68°F to 77°F), with excursions permitted between 15°C and 30°C (59°F and 86°F). Store BELBUCA securely and dispose of properly.

17 PATIENT COUNSELING INFORMATION

Advise the patient to read the FDA-approved patient labeling (Medication Guide).

Storage and Disposal

Because of the risks associated with accidental ingestion, misuse, and abuse, advise patients to store BELBUCA securely, out of sight and reach of children, and in a location not accessible by others, including visitors to the home. Inform patients that leaving BELBUCA unsecured can pose a deadly risk to others in the home [see Warnings and Precautions (5.1, 5.2), Drug Abuse and Dependence (9.2)].

Advise patients and caregivers that when medicines are no longer needed, they should be disposed of promptly. Expired, unwanted, or unused BELBUCA should be disposed of by removing the BELBUCA film from the foil packaging and flushing the unused medication down the toilet (if a drug take-back option is not readily available). Inform patients that they can visit www.fda.gov/drugdisposal for a complete list of medicines recommended for disposal by flushing, as well as additional information on disposal of unused medicines.

Addiction, Abuse, and Misuse

Inform patients that the use of BELBUCA, even when taken as recommended, can result in addiction, abuse, and misuse, which could lead to overdose and death [see Warnings and Precautions (5.1)]. Instruct patients not to share BELBUCA with others and to take steps to protect BELBUCA from theft or misuse.

Life-Threatening Respiratory Depression

Inform patients of the risk of life-threatening respiratory depression, including information that the risk is greatest when starting BELBUCA or when the dosage is increased, and that it can occur even at recommended doses.

Educate patients and caregivers on how to recognize respiratory depression and emphasize the importance of calling 911 or getting emergency medical help right away in the event of a known or suspected overdose [see Warnings and Precautions (5.2)].

Accidental Exposure

Inform patients that accidental exposure, especially in children, may result in respiratory depression or death [see Warnings and Precautions (5.2)].

Interactions with Benzodiazepines and Other CNS Depressants

Inform patients and caregivers that potentially fatal additive effects may occur if BELBUCA is used with benzodiazepines or other CNS depressants, including alcohol (e.g., non-benzodiazepine sedative/hypnotics, anxiolytics, tranquilizers, muscle relaxants, general anesthetics, antipsychotics, gabapentinoids [gabapentin or pregabalin], and other opioids), and not to use these concomitantly unless supervised by a healthcare provider [see Warnings and Precautions (5.3), Drug Interactions (7)].

Interaction with Benzodiazepines

Warn patients that it is extremely dangerous to self-administer benzodiazepines while taking BELBUCA and warn patients to use benzodiazepines concurrently with BELBUCA only as directed by their physician [see Drug Interactions (7)].

Patient Access to an Opioid Overdose Reversal Agent for the Emergency Treatment of Opioid Overdose

Inform patients and caregivers about opioid overdose reversal agents (e.g., naloxone, nalmefene). Discuss the importance of having access to an opioid overdose reversal agent, especially if the patient has risk factors for overdose (e.g., concomitant use of CNS depressants, a history of opioid use disorder, or prior opioid overdose) or if there are household members (including children) or other close contacts at risk for accidental ingestion or opioid overdose.

Discuss with the patient the options for obtaining an opioid overdose reversal agent (e.g., prescription, over-the-counter, or as part of a community-based program) [see Dosage and Administration (2.2), Warnings and Precautions (5.3)].

Educate patients and caregivers on how to recognize the signs and symptoms of an overdose.

Explain to patients and caregivers that effects of opioid overdose reversal agents like naloxone and nalmefene are temporary, and that they must call 911 or get emergency medical help right away in all cases of known or suspected opioid overdose, even if an opioid overdose reversal agent is administered [see Overdosage (10)].

Advise patients and caregivers:

- how to treat with the overdose reversal agent in the event of an opioid overdose.
- tot tell family and friends about their overdose reversal agent and to keep it in a place where family and friends can access it in an emergency.
- tot read the Patient Information (or other educational material) that will come with their overdose reversal agent. Emphasize the importance of doing this before an opioid emergency happens, so the patient and caregiver will know what to do.

Hyperalgesia and Allodynia

Inform patients and caregivers not to increase opioid dosage without first consulting a clinician. Advise patients to seek medical attention if they experience symptoms of hyperalgesia, including worsening pain, increased sensitivity to pain, or new pain [see Warnings and Precautions (5.6), Adverse Reactions (6.2)].

Serotonin Syndrome

Inform patients that BELBUCA could cause a rare but potentially life-threatening condition called serotonin syndrome resulting from concomitant administration of serotonergic drugs. Warn patients of the symptoms of serotonin syndrome and to seek medical attention right away if symptoms develop. Instruct patients to inform their physicians if they are taking, or plan to take, serotonergic medications [see Drug Interactions (7)].

Important Administration Instructions

Instruct patients how to properly use BELBUCA, including the following:

- To carefully follow instructions for the application of BELBUCA and to avoid eating or drinking until it dissolves.
- Advise patients that, after BELBUCA has completely dissolved in the oral mucosa, to take a sip of water, swish it gently around their teeth and gums, and swallow. Advise patients to wait for at least one hour after taking BELBUCA before brushing teeth [see Warnings and Precautions (5.14)].
- To apply BELBUCA once daily, or every twelve (12) hours at the same time or times each day.
- To avoid applying BELBUCA to areas of the mouth with any open sores or lesions.
- To not use BELBUCA if the pouch seal is broken or the buccal film is cut, damaged, or changed in any way.
- Refer patients to dental care services and encourage them to have regular dental checkups while taking BELBUCA. Instruct patients to inform their dentist that they have started therapy on BELBUCA [see Warnings and Precautions (5.14)].

Important Discontinuation Instructions

In order to avoid developing withdrawal symptoms, instruct patients not to discontinue BELBUCA without first discussing a tapering plan with the prescriber [see Dosage and Administration (2.5)].

Driving or Operating Heavy Machinery

Inform patients that BELBUCA may impair the ability to perform potentially hazardous activities such as driving a car or operating heavy machinery. Advise patients not to perform such tasks until they know how they will react to the medication [see Warnings and Precautions (5.18)].

Constipation

Advise patients of the potential for severe constipation, including management instructions and when to seek medical attention [see Adverse Reactions (6), Clinical Pharmacology (12.2)].

Adrenal Insufficiency

Inform patients that BELBUCA could cause adrenal insufficiency, a potentially life-threatening condition. Adrenal insufficiency may present with non-specific symptoms and signs such as nausea, vomiting, anorexia, fatigue, weakness, dizziness, and low blood pressure. Advise patients to seek medical attention if they experience a constellation of these symptoms [see Warnings and Precautions (5.8)].

Hypotension

Inform patients that BELBUCA may cause orthostatic hypotension and syncope. Instruct patients how to recognize symptoms of low blood pressure and how to reduce the risk of serious consequences should hypotension occur (e.g., sit or lie down, carefully rise from a sitting or lying position) [see Warnings and Precautions (5.9)].

Anaphylaxis

Inform patients that anaphylaxis has been reported with ingredients contained in BELBUCA. Advise patients how to recognize such a reaction and when to seek medical attention [see Warnings and Precautions (5.16)].

Pregnancy

Neonatal Opioid Withdrawal Syndrome

Inform female patients of reproductive potential that use of BELBUCA for an extended period of time during pregnancy can result in neonatal opioid withdrawal syndrome, which may be life-threatening if not recognized and treated [see Warnings and Precautions (5.4), Use in Specific Populations (8.1)].

Embryofetal Toxicity

Inform female patients of reproductive potential that BELBUCA can cause fetal harm and to inform their healthcare provider of a known or suspected pregnancy [see Use in Specific Populations (8.1)].

Lactation

Advise patients that breastfeeding is not recommended during treatment with BELBUCA [see Use in Specific Populations (8.2)].

Healthcare professionals can telephone Collegium Pharmaceutical, Inc. at 1-855-331-5615 or access www.BELBUCA.com for information on this product.

Distributed by:
Collegium Pharmaceutical, Inc.
Stoughton, MA 02072 USA

BELBUCA is a trademark of BioDelivery Sciences International, Inc., a wholly owned subsidiary of Collegium Pharmaceutical, Inc.

©2025 BioDelivery Sciences International, Inc. All rights reserved.

BEL-001-PI-XX2026

Medication Guide
BELBUCA® (bel-BUE-kuh)
(buprenorphine buccal film), CIII

BELBUCA is:

- A strong prescription pain medicine that contains an opioid (narcotic) that is used to manage severe and persistent pain that requires an extended treatment period with a daily opioid pain medicine when other pain medicines do not treat your pain well enough or you cannot tolerate them.
- A long-acting opioid pain medicine that can put you at risk for overdose and death. Even if you take your dose correctly as prescribed, you are at risk for opioid addiction, abuse, and misuse that can lead to death.
- Not to be taken on an "as needed" basis.

Important information about BELBUCA:

- Get emergency help or call 911 right away if you take too much BELBUCA (overdose). When you first start taking BELBUCA, when your dose is changed, or if you take too much (overdose), serious or life-threatening breathing problems that can lead to death may occur. Ask your healthcare provider about medicines like naloxone or nalmefene that can be used in an emergency to reverse an opioid overdose.
- Taking BELBUCA with other opioid medicines, benzodiazepines, gabapentinioids (gabapentin or pregabalin), alcohol, or other central nervous system depressants (including street drugs) can cause severe drowsiness, decreased awareness, breathing problems, coma, and death.
- Never give anyone else your BELBUCA. They could die from taking it. Selling or giving away BELBUCA is against the law.
- Store BELBUCA securely, out of sight and reach of children, and in a location not accessible by others, including visitors to the home.

Do not use BELBUCA if you have:

- severe asthma, trouble breathing, or other lung problems.
- a bowel blockage or have narrowing of the stomach or intestines.

Before taking BELBUCA, tell your healthcare provider if you have a history of:

- head injury, seizures
- liver, kidney, thyroid problems
- problems urinating
- tooth problems, including a history of cavities.

- heart rhythm problems (long QT syndrome)
- pancreas or gallbladder problems
- abuse of street or prescription drugs, alcohol addiction, opioid overdose, or mental health problems

Tell your healthcare provider if you are:

- noticing your pain getting worse. If your pain gets worse after you take BELBUCA, do not take more of BELBUCA without first talking to your healthcare provider. Talk to your healthcare provider if the pain that you have increases, if you feel more sensitive to pain, or if you have new pain after taking BELBUCA.
- pregnant or planning to become pregnant. Use of BELBUCA for an extended period of time during pregnancy can cause withdrawal symptoms in your newborn baby that could be life-threatening if not recognized and treated.
- breastfeeding. Not recommended during treatment with BELBUCA. It may harm your baby.
- living in a household where there are small children or someone who has abused street or prescription drugs.
- taking prescription or over-the-counter medicines, vitamins, or herbal supplements. Taking BELBUCA with certain other medicines can cause serious side effects and could lead to death.

When taking BELBUCA:

- Do not change your dose. Apply BELBUCA exactly as prescribed by your healthcare provider. Use the lowest effective dose possible for the shortest time needed.
- See the detailed Instructions for Use for information about how to apply BELBUCA.
- Do not apply BELBUCA if the package seal is broken or the film is cut, damaged, or changed in any way.
- After the film has adhered to your cheek, avoid eating or drinking until the film has completely dissolved, usually within 30 minutes.
- After BELBUCA is completely dissolved, rinse your mouth with water and swallow. Wait for at least one hour before brushing teeth.
- Report any problems with your teeth immediately to your healthcare provider and schedule an appointment with a dentist. Tell your dentist that you have started taking BELBUCA. Avoid touching or moving the buccal film with your tongue or fingers.
- Do not chew, swallow, snort or inject BELBUCA. This will result in uncontrolled delivery of buprenorphine and may cause you to overdose and die.
- Call your healthcare provider if the dose you are using does not control your pain.
- Do not stop using BELBUCA without talking to your healthcare provider.
- Dispose of expired, unwanted, or unused BELBUCA by removing the BELBUCA film from the foil packaging, and promptly flushing down the toilet (if a drug takeback option is not readily available). Visit www.fda.gov/drugdisposal for additional information on disposal of unused medicines.

While using BELBUCA DO NOT:

- Drive or operate heavy machinery, until you know how BELBUCA affects you. BELBUCA can make you sleepy, dizzy, or lightheaded.
- Drink alcohol or use prescription or over-the-counter medicines containing alcohol. Using products containing alcohol during treatment with BELBUCA may cause you to overdose and die.

The possible side effects of BELBUCA are:

- nausea, constipation, headache, vomiting, dizziness, and sleepiness. Call your healthcare provider if you have any of these symptoms and they are severe.

Get emergency medical help or call 911 right away if you have:

- trouble breathing, shortness of breath, fast heartbeat, chest pain, swelling of your face, tongue or throat, extreme drowsiness, light-headedness when changing positions, feeling faint, agitation, high body temperature, trouble walking, stiff muscles, or mental changes such as confusion.

These are not all the possible side effects of BELBUCA. Call your healthcare provider for medical advice about side effects. You may report side effects to FDA at 1-800-FDA-1088. For more information go to dailymed.nlm.nih.gov
Manufactured for: Collegium Pharmaceutical, Inc., Stoughton, MA 02072 www.BELBUCA.com or call 855-331-5615.

This Medication Guide has been approved by the U.S. Food and Drug Administration.

Revised: December 2025

Instructions for Use

BELBUCA (bel-BUE-kuh)
(buprenorphine buccal film), CIII

Before you use BELBUCA buccal film, it is important that you read the Medication Guide and these Patient Instructions for Use so that you use BELBUCA the right way. Ask your healthcare provider or pharmacist if you have any questions about the right way to use BELBUCA.

Important:

- BELBUCA buccal film is sealed in a foil package. Do not open the package until ready to use. After opening, use the entire BELBUCA buccal film right away.
- Do not apply BELBUCA buccal film if the package seal is broken or the film is cut, damaged, or changed in any way.
- BELBUCA buccal film is available in different strengths. Make sure you have the strength that has been prescribed for you.
- Avoid placing BELBUCA buccal film to areas of the mouth with any open sores or lesions.

Open the BELBUCA package:

- Hold the foil package as shown below (see Figure A). Fold along the dotted line at the top of the foil package.
  Figure A
- Keep folded and tear down or cut with scissors at the notch in the direction of the scissors on the dotted line (see Figure B). Tear all the way to the bottom. Be careful to avoid cutting and damaging the BELBUCA buccal film when using scissors.
  Figure B
- Remove BELBUCA film from the foil package (see Figure C).
  Figure C

Use BELBUCA buccal film as follows:

1. Use your tongue to wet the inside of your cheek or rinse your mouth with water to moisten the area in your mouth before you place BELBUCA.
2. Hold the BELBUCA buccal film with clean, dry fingers with the yellow side facing up (see Figure D).
  Figure D
3. Using a finger, place the yellow side of the BELBUCA buccal film against the inside of your moistened cheek. Press and hold the BELBUCA buccal film in place for 5 seconds and then take your finger away (see Figure E).
  Figure E
4. The BELBUCA buccal film will stick to the inside of your cheek (see Figure F).
  Figure F
5. Leave the BELBUCA buccal film in place until it has completely dissolved, usually within 30 minutes after you apply it.
  - Avoid eating food or drinking liquids until BELBUCA buccal film has dissolved.
  - Avoid touching or moving BELBUCA buccal film with your tongue or finger after it is in place.
  - Do not chew or swallow BELBUCA.
  - After BELBUCA is completely dissolved, rinse your mouth with water and swallow. Wait at least one hour before brushing your teeth.

These Instructions for Use have been approved by the U.S. Food and Drug Administration.

For more information call Collegium Pharmaceutical, Inc. at 855-331-5615.

Manufactured for:

Collegium Pharmaceutical, Inc., Stoughton, MA 02072

BELBUCA is a trademark of BioDelivery Sciences International, Inc., a wholly owned subsidiary of Collegium Pharmaceutical, Inc.

©2025 BioDelivery Sciences International, Inc. All rights reserved.

BEL-001-MG-XX2025

PRINCIPAL DISPLAY PANEL - 75 mcg Film Pouch Box

NDC 59385-021-60

CIII

Belbuca®
(buprenorphine buccal film)

Push To
Open

75 mcg

60 pouches containing 1 buccal film each

Use entire film. Do not cut, tear, chew or swallow film.

Keep Belbuca out of sight and reach of children.
Children who accidentally take Belbuca will
need emergency medical care.

Dispense the enclosed
Medication Guide
to each patient.

Rx only

PRINCIPAL DISPLAY PANEL - 150 mcg Film Pouch Box

NDC 59385-022-60

CIII

Belbuca®
(buprenorphine buccal film)

Push To
Open

150 mcg

60 pouches containing 1 buccal film each

Use entire film. Do not cut, tear, chew or swallow film.

Keep Belbuca out of sight and reach of children.
Children who accidentally take Belbuca will
need emergency medical care.

Dispense the enclosed
Medication Guide
to each patient.

Rx only

PRINCIPAL DISPLAY PANEL - 300 mcg Film Pouch Box

NDC 59385-023-60

CIII

Belbuca®
(buprenorphine buccal film)

Push To
Open

300 mcg

60 pouches containing 1 buccal film each

Use entire film. Do not cut, tear, chew or swallow film.

Keep Belbuca out of sight and reach of children.
Children who accidentally take Belbuca will
need emergency medical care.

Dispense the enclosed
Medication Guide
to each patient.

Rx only

PRINCIPAL DISPLAY PANEL - 450 mcg Film Pouch Box

NDC 59385-024-60

CIII

Belbuca®
(buprenorphine buccal film)

Push To
Open

450 mcg

60 pouches containing 1 buccal film each

Use entire film. Do not cut, tear, chew or swallow film.

Keep Belbuca out of sight and reach of children.
Children who accidentally take Belbuca will
need emergency medical care.

Dispense the enclosed
Medication Guide
to each patient.

Rx only

PRINCIPAL DISPLAY PANEL - 600 mcg Film Pouch Box

NDC 59385-025-60

CIII

Belbuca®
(buprenorphine buccal film)

Push To
Open

600 mcg

60 pouches containing 1 buccal film each

Use entire film. Do not cut, tear, chew or swallow film.

Keep Belbuca out of sight and reach of children.
Children who accidentally take Belbuca will
need emergency medical care.

Dispense the enclosed
Medication Guide
to each patient.

Rx only

PRINCIPAL DISPLAY PANEL - 750 mcg Film Pouch Box

NDC 59385-026-60

CIII

Belbuca®
(buprenorphine buccal film)

Push To
Open

750 mcg

60 pouches containing 1 buccal film each

Use entire film. Do not cut, tear, chew or swallow film.

Keep Belbuca out of sight and reach of children.
Children who accidentally take Belbuca will
need emergency medical care.

Dispense the enclosed
Medication Guide
to each patient.

Rx only

PRINCIPAL DISPLAY PANEL - 900 mcg Film Pouch Box

NDC 59385-027-60

CIII

Belbuca®
(buprenorphine buccal film)

Push To
Open

900 mcg

60 pouches containing 1 buccal film each

Use entire film. Do not cut, tear, chew or swallow film.

Keep Belbuca out of sight and reach of children.
Children who accidentally take Belbuca will
need emergency medical care.

Dispense the enclosed
Medication Guide
to each patient.

Rx only